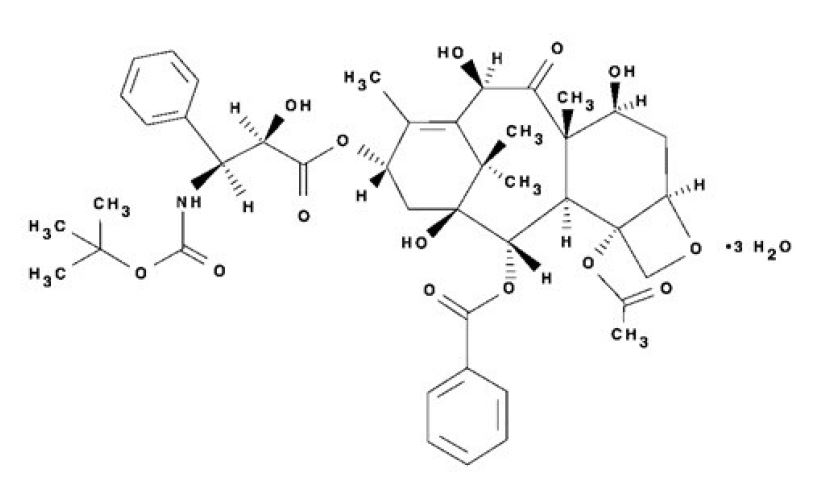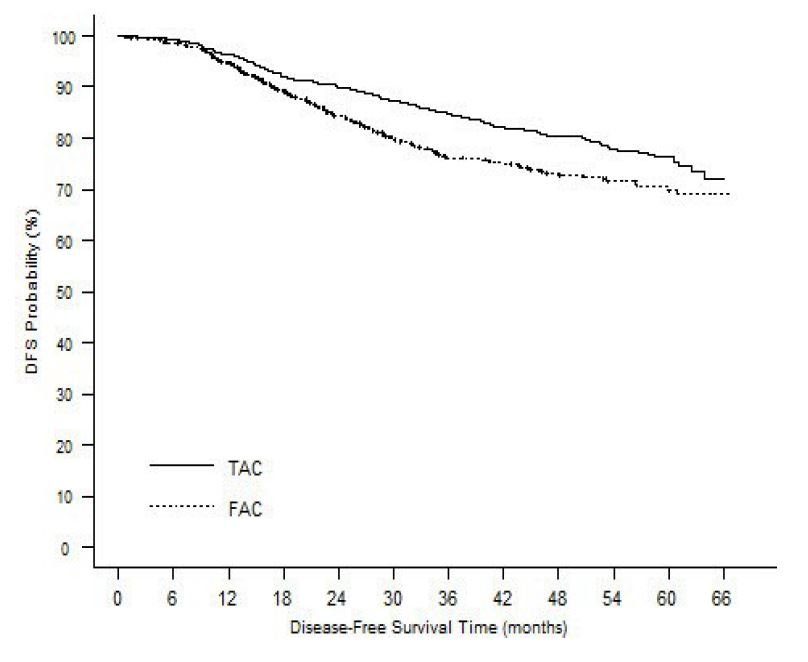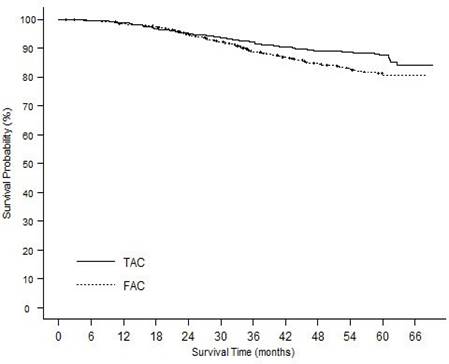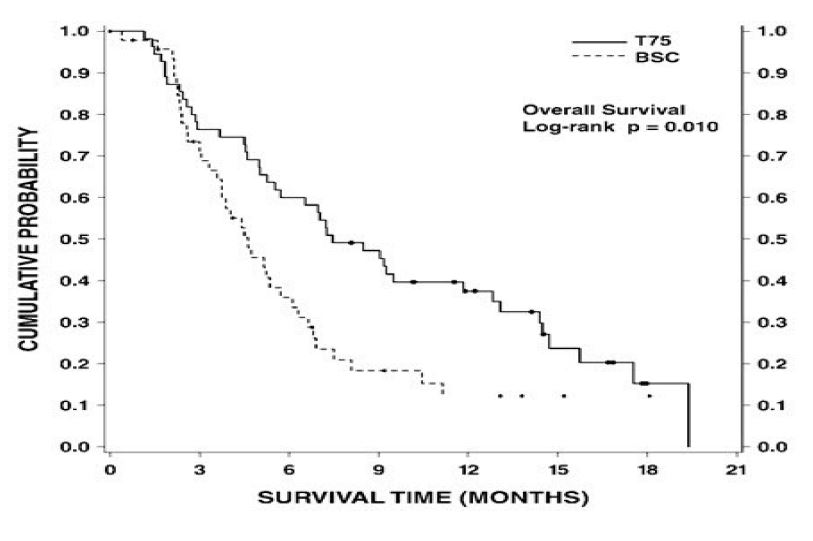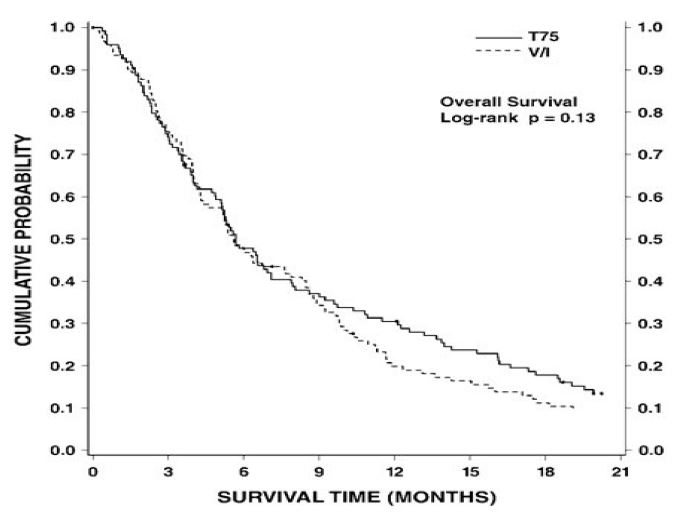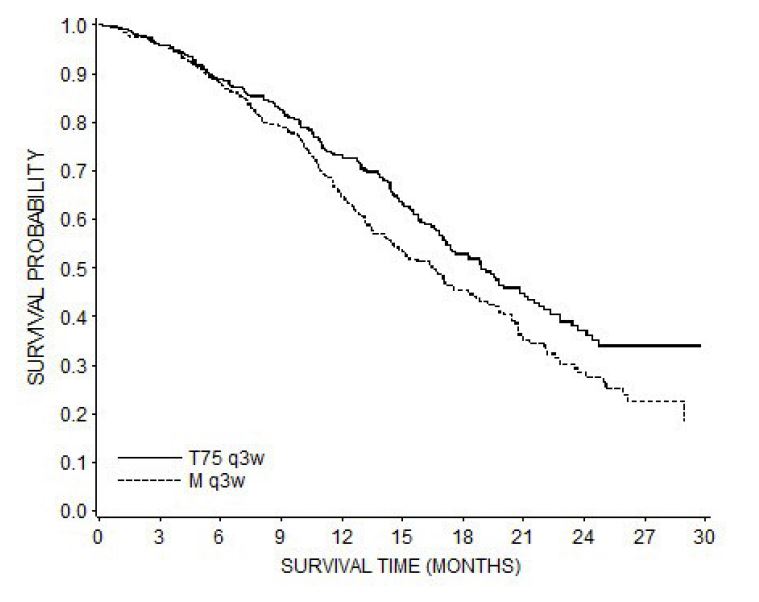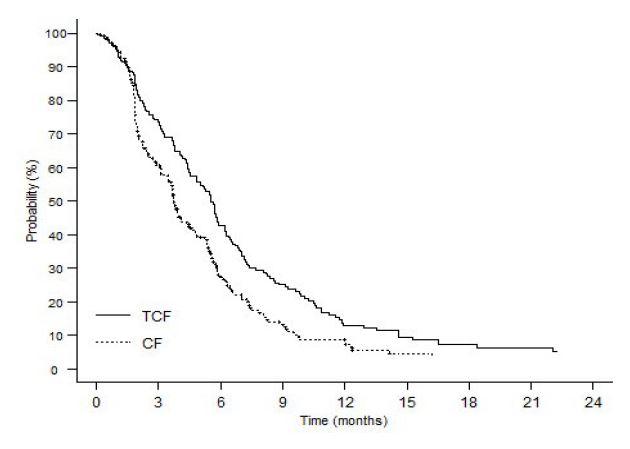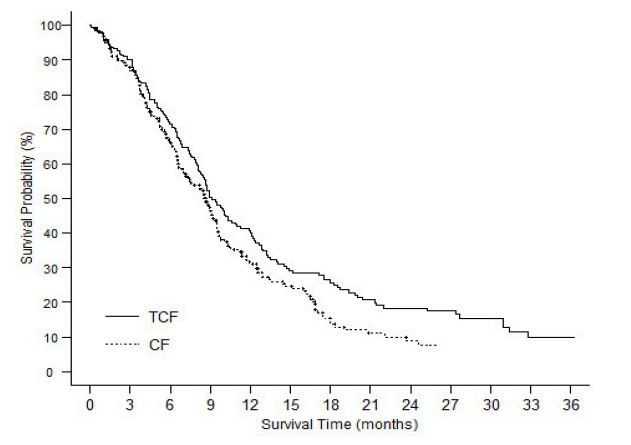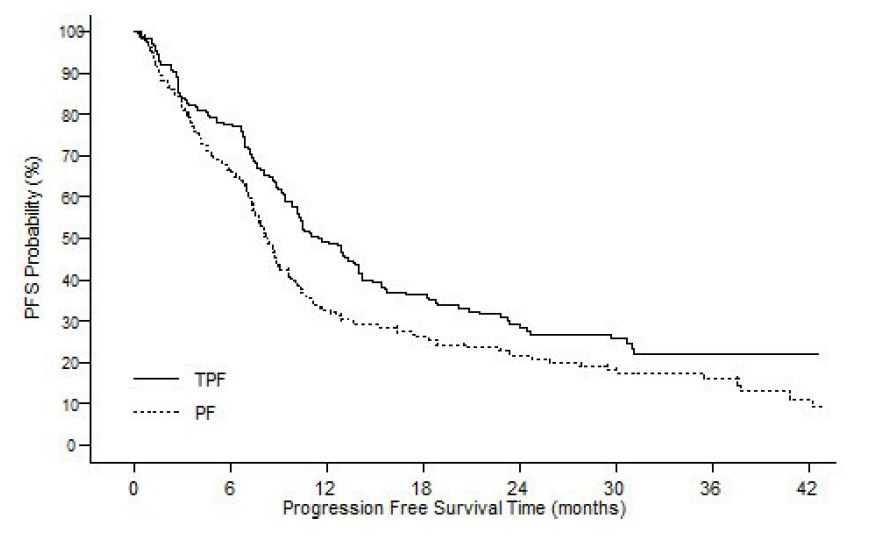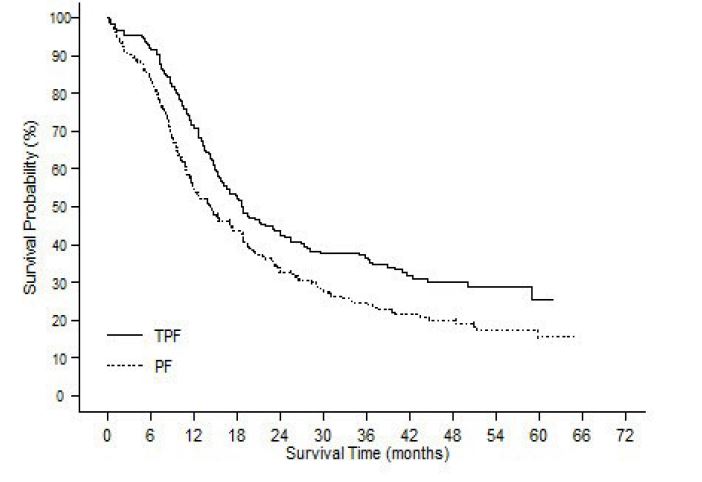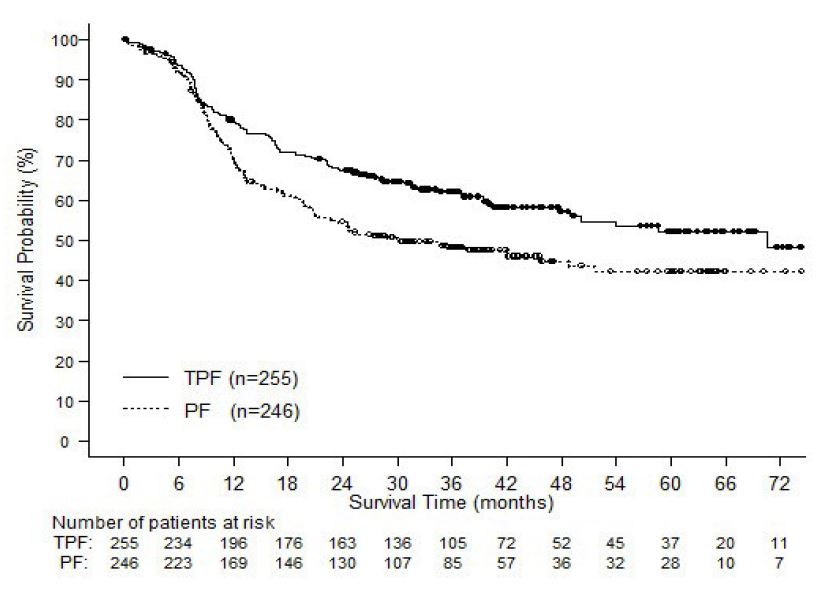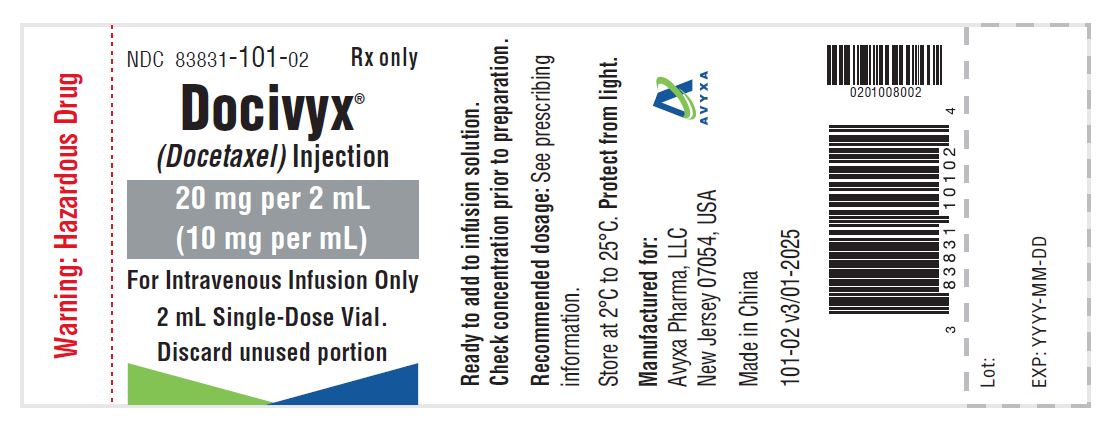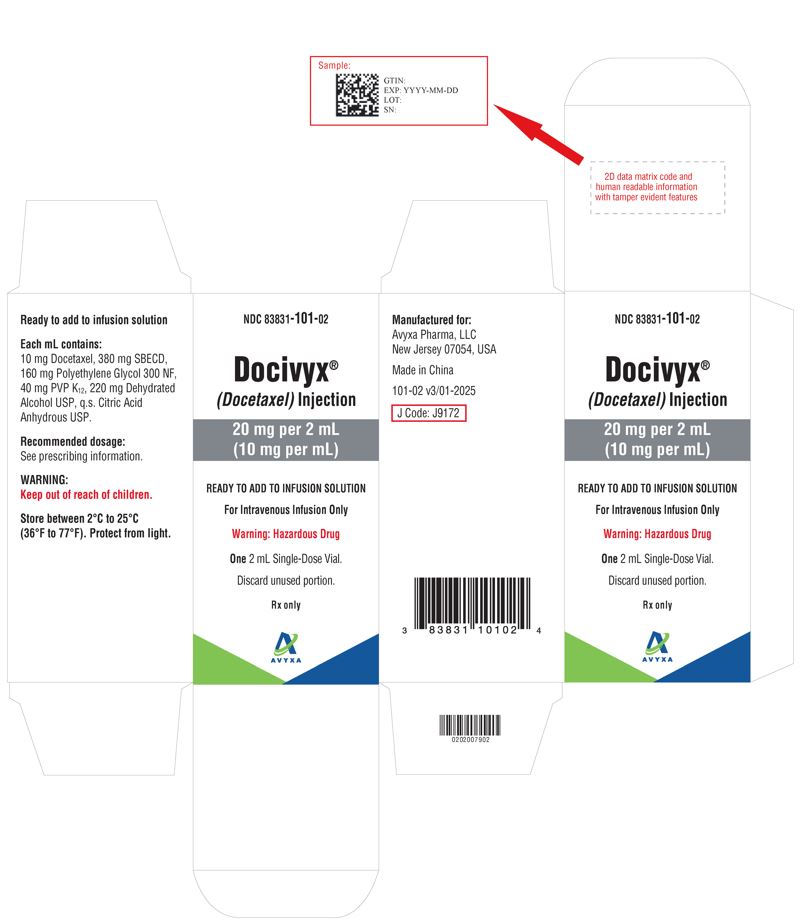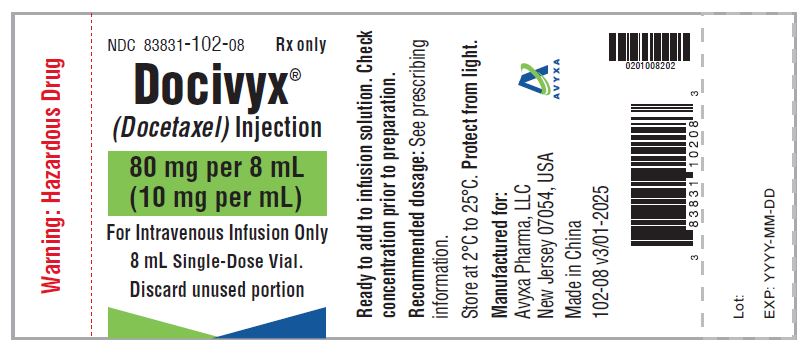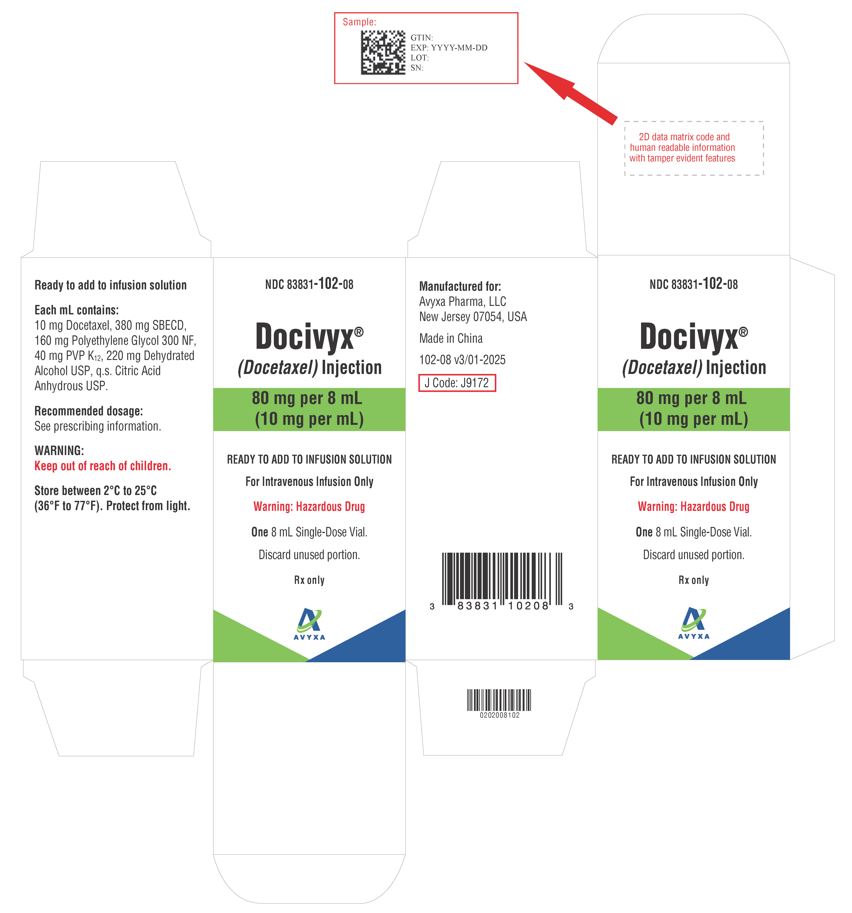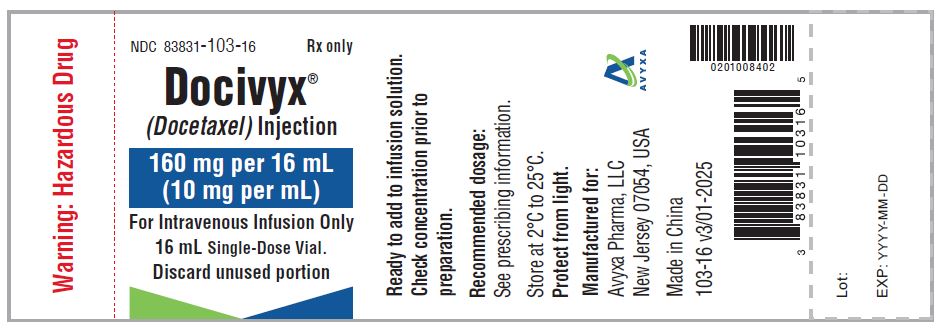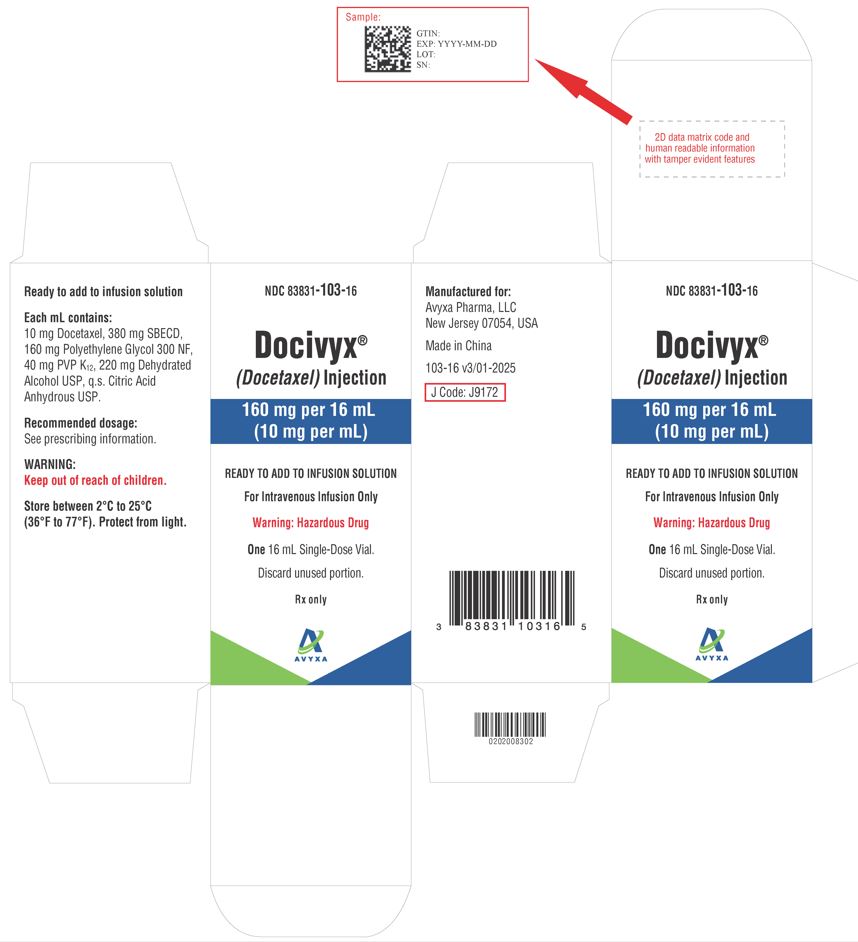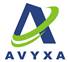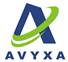 DRUG LABEL: DOCIVYX
NDC: 83831-101 | Form: INJECTION, SOLUTION
Manufacturer: Avyxa Pharma, LLC
Category: prescription | Type: HUMAN PRESCRIPTION DRUG LABEL
Date: 20250715

ACTIVE INGREDIENTS: DOCETAXEL 20 mg/2 mL
INACTIVE INGREDIENTS: POLYETHYLENE GLYCOL 300; POVIDONE; ALCOHOL; BETADEX SULFOBUTYL ETHER SODIUM; ANHYDROUS CITRIC ACID

HIGHLIGHTS OF PRESCRIBING INFORMATION

These highlights do not include all the information needed to use DOCIVYX safely and effectively. See full prescribing information for DOCIVYX.
DOCIVYX® (docetaxel) injection, for intravenous use
Initial U.S. Approval: 1996

BOXED WARNING

WARNING: TOXIC DEATHS, HEPATOTOXICITY, NEUTROPENIA, HYPERSENSITIVITY REACTIONS, and FLUID RETENTION

See full prescribing information for complete boxed warning.

- Treatment-related mortality increases with abnormal liver function, at higher doses, and in patients with NSCLC and prior platinum-based therapy receiving DOCIVYX at 100 mg/m^2(5.1)
- Avoid use of DOCIVYX if bilirubin > ULN, or if AST and/or ALT >1.5 × ULN concomitant with alkaline phosphatase >2.5 × ULN. LFT elevations increase risk of severe or life-threatening complications. Obtain LFTs before each treatment cycle (5.2)
- Do not administer DOCIVYX to patients with neutrophil counts <1500 cells/mm^3. Obtain frequent blood counts to monitor for neutropenia (4, 5.3)
- Severe hypersensitivity, including fatal anaphylaxis, has been reported in patients who received dexamethasone premedication. Severe reactions require immediate discontinuation of DOCIVYX and administration of appropriate therapy (5.5)
- Contraindicated if history of severe hypersensitivity reactions to DOCIVYX (4)
- Severe fluid retention may occur despite dexamethasone (5.6)

1 INDICATIONS AND USAGE

DOCIVYX is a microtubule inhibitor indicated for:

- Breast Cancer (BC): single agent for locally advanced or metastatic BC after chemotherapy failure; and with doxorubicin and cyclophosphamide as adjuvant treatment of operable node-positive BC (1.1)
- Non-small Cell Lung Cancer (NSCLC):single agent for locally advanced or metastatic NSCLC after platinum therapy failure; and with cisplatin for unresectable, locally advanced or metastatic untreated NSCLC (1.2)
- Castration-Resistant Prostate Cancer (CRPC): with prednisone in metastatic CRPC (1.3)
- Gastric Adenocarcinoma (GC): with cisplatin and fluorouracil for untreated, advanced GC, including the gastroesophageal junction (1.4)
- Squamous Cell Carcinoma of the Head and Neck (SCCHN): with cisplatin and fluorouracil for induction treatment of locally advanced SCCHN (1.5)

2 DOSAGE AND ADMINISTRATION

Administer in a facility equipped to manage possible complications (e.g., anaphylaxis). Administer intravenously (IV) over 1 hr every 3 weeks. PVC equipment is not recommended. Use only a 21-gauge needle to withdraw DOCIVYX from the vial.

- BC locally advanced or metastatic: 60 mg/m^2to 100 mg/m^2single agent (2.1)
- BC adjuvant: 75 mg/m^2administered 1 hour after doxorubicin 50 mg/m^2and cyclophosphamide 500 mg/m^2every 3 weeks for 6 cycles (2.1)
- NSCLC: after platinum therapy failure: 75 mg/m^2single agent (2.2)
- NSCLC: chemotherapy naive: 75 mg/m^2followed by cisplatin 75 mg/m^2(2.2)
- CRPC: 75 mg/m^2with 5 mg prednisone twice a day continuously (2.3)
- GC: 75 mg/m^2followed by cisplatin 75 mg/m^2(both on day 1 only) followed by fluorouracil 750 mg/m^2per day as a 24-hour IV (days 1-5), starting at end of cisplatin infusion (2.4)
- SCCHN: 75 mg/m^2followed by cisplatin 75 mg/m^2IV (day 1), followed by fluorouracil 750 mg/m^2per day as a 24-hr IV (days 1–5), starting at end of cisplatin infusion; for 4 cycles (2.5)
- SCCHN: 75 mg/m^2followed by cisplatin 100 mg/m^2IV (day 1), followed by fluorouracil 1000 mg/m^2per day as a 24-hr IV (days 1–4); for 3 cycles (2.5)

For all patients:

- Premedicate with oral corticosteroids (2.6)
- Adjust dose as needed (2.7)

3 DOSAGE FORMS AND STRENGTHS

- Injection: Single-dose vials 20 mg/2 mL, 80 mg/8 mL and 160 mg/16 mL (3)

4 CONTRAINDICATIONS

- Hypersensitivity to docetaxel (4)
- Neutrophil counts of <1500 cells/mm ^3(4)

5 WARNINGS AND PRECAUTIONS

- Second primary malignancies: In patients treated with DOCIVYX-containing regimens, monitor for delayed AML, MDS, NHL, and renal cancer. (5.7)
- Cutaneous reactions: Reactions including erythema of the extremities with edema followed by desquamation may occur. Severe cutaneous adverse reactions have been reported. Severe skin toxicity may require dose adjustment or permanent treatment discontinuation. (5.8)
- Neurologic reactions: Reactions including paresthesia, dysesthesia, and pain may occur. Severe neurosensory symptoms require dose adjustment or discontinuation if persistent. (5.9)
- Eye disorders: Cystoid macular edema (CME) has been reported and requires treatment discontinuation. (5.10)
- Asthenia: Severe asthenia may occur and may require treatment discontinuation. (5.11)
- Embryo-fetal toxicity: Can cause fetal harm. Advise patients of the potential risk to a fetus and to use effective contraception. (5.12, 8.1,8.3)
- Alcohol content: The alcohol content in a dose of DOCIVYX may affect the central nervous system. This may include impairment of a patient's ability to drive or use machines immediately after infusion. (5.13)
- Tumor lysis syndrome: Tumor lysis syndrome has been reported. Patients at risk should be well hydrated and closely monitored during treatment. (5.14)

6 ADVERSE REACTIONS

Most common adverse reactions across all DOCIVYX indications are infections, neutropenia, anemia, febrile neutropenia, hypersensitivity, thrombocytopenia, neuropathy, dysgeusia, dyspnea, constipation, anorexia, nail disorders, fluid retention, asthenia, pain, nausea, diarrhea, vomiting, mucositis, alopecia, skin reactions, and myalgia. (6)

To report SUSPECTED ADVERSE REACTIONS, contact Avyxa Pharma,LLC at 1-888-520-0954 or FDA at 1-800-FDA-1088 or www.fda.gov/medwatch

7 DRUG INTERACTIONS

- Cytochrome P450 3A4 inducers, inhibitors, or substrates: May alter docetaxel metabolism. (7)

8 USE IN SPECIFIC POPULATIONS

- Lactation: Advise women not to breastfeed. (8.2)
- Females and Males of Reproductive Potential: Verify pregnancy status of females prior to initiation of DOCIVYX. (8.3)

FULL PRESCRIBING INFORMATION

BOXED WARNING

WARNING: TOXIC DEATHS, HEPATOTOXICITY, NEUTROPENIA, HYPERSENSITIVITY REACTIONS, and FLUID RETENTION

Treatment-related mortality associated with DOCIVYX is increased in patients with abnormal liver function, in patients receiving higher doses, and in patients with non-small cell lung carcinoma and a history of prior treatment with platinum-based chemotherapy who receive DOCIVYX as a single agent at a dose of 100 mg/m^2 [see Warnings and Precautions (5.1)].

Avoid the use of DOCIVYX in patients with bilirubin > upper limit of normal (ULN), or to patients with AST and/or ALT >1.5 × ULN concomitant with alkaline phosphatase >2.5 × ULN. Patients with elevations of bilirubin or abnormalities of transaminase concurrent with alkaline phosphatase are at increased risk for the development of severe neutropenia, febrile neutropenia, infections, severe thrombocytopenia, severe stomatitis, severe skin toxicity, and toxic death. Patients with isolated elevations of transaminase >1.5 × ULN also had a higher rate of febrile neutropenia. Measure bilirubin, AST or ALT, and alkaline phosphatase prior to each cycle of DOCIVYX [see Warnings and Precautions (5.2)].

Do not administer DOCIVYX to patients with neutrophil counts of <1500 cells/mm^3. Monitor blood counts frequently as neutropenia may be severe and result in infection. [see Warnings and Precautions (5.3)].

Do not administer DOCIVYX to patients who have a history of severe hypersensitivity reactions to DOCIVYX [see Contraindications (4)]. Severe hypersensitivity reactions have been reported in patients despite dexamethasone premedication. Hypersensitivity reactions require immediate discontinuation of the DOCIVYX infusion and administration of appropriate therapy [see Warnings and Precautions (5.5)].

Severe fluid retention occurred in 6.5% (6/92) of patients despite use of dexamethasone premedication. It was characterized by one or more of the following events: poorly tolerated peripheral edema, generalized edema, pleural effusion requiring urgent drainage, dyspnea at rest, cardiac tamponade, or pronounced abdominal distention (due to ascites) [see Warnings and Precautions (5.6)].

1 INDICATIONS AND USAGE

1.1 Breast Cancer

DOCIVYX is indicated for the treatment of patients with locally advanced or metastatic breast cancer after failure of prior chemotherapy.

DOCIVYX in combination with doxorubicin and cyclophosphamide is indicated for the adjuvant treatment of patients with operable node-positive breast cancer.

1.2 Non-small Cell Lung Cancer

DOCIVYX as a single agent is indicated for the treatment of patients with locally advanced or metastatic non-small cell lung cancer after failure of prior platinum-based chemotherapy.

DOCIVYX in combination with cisplatin is indicated for the treatment of patients with unresectable, locally advanced or metastatic non-small cell lung cancer who have not previously received chemotherapy for this condition.

1.3 Prostate Cancer

DOCIVYX in combination with prednisone is indicated for the treatment of patients with metastatic CRPC.

1.4 Gastric Adenocarcinoma

DOCIVYX in combination with cisplatin and fluorouracil is indicated for the treatment of patients with advanced gastric adenocarcinoma, including adenocarcinoma of the gastroesophageal junction, who have not received prior chemotherapy for advanced disease.

1.5 Head and Neck Cancer

DOCIVYX in combination with cisplatin and fluorouracil is indicated for the induction treatment of patients with locally advanced squamous cell carcinoma of the head and neck (SCCHN).

2 DOSAGE AND ADMINISTRATION

For all indications, toxicities may warrant dosage adjustments [see Dosage and Administration (2.7)]. Administer in a facility equipped to manage possible complications (e.g., anaphylaxis).

2.1 Breast Cancer

- For locally advanced or metastatic breast cancer after failure of prior chemotherapy, the recommended dose of DOCIVYX is 60 mg/m^2to 100 mg/m^2administered intravenously over 1 hour every 3 weeks.
- For the adjuvant treatment of operable node-positive breast cancer, the recommended DOCIVYX dose is 75 mg/m^2administered 1 hour after doxorubicin 50 mg/m^2and cyclophosphamide 500 mg/m^2every 3 weeks for 6 courses. Prophylactic G-CSF may be used to mitigate the risk of hematological toxicities [see Dosage and Administration (2.7)].

2.2 Non-small Cell Lung Cancer

- For treatment after failure of prior platinum-based chemotherapy, DOCIVYX was evaluated as monotherapy, and the recommended dose is 75 mg/m^2administered intravenously over 1 hour every 3 weeks. A dose of 100 mg/m^2in patients previously treated with chemotherapy was associated with increased hematologic toxicity, infection, and treatment-related mortality in randomized controlled trials [see Boxed Warning, Dosage and Administration (2.7), Warnings and Precautions (5), Clinical Studies (14)].
- For chemotherapy-naive patients, DOCIVYX was evaluated in combination with cisplatin. The recommended dose of DOCIVYX is 75 mg/m^2administered intravenously over 1 hour immediately followed by cisplatin 75 mg/m^2over 30–60 minutes every 3 weeks [see Dosage and Administration (2.7)].

2.3 Prostate Cancer

- For metastatic CRPC, the recommended dose of DOCIVYX is 75 mg/m^2every 3 weeks as a 1-hour intravenous infusion. Prednisone 5 mg orally twice daily is administered continuously [see Dosage and Administration (2.7)].

2.4 Gastric Adenocarcinoma

- For gastric adenocarcinoma, the recommended dose of DOCIVYX is 75 mg/m^2as a 1-hour intravenous infusion, followed by cisplatin 75 mg/m^2, as a 1 to 3 hour intravenous infusion (both on day 1 only), followed by fluorouracil 750 mg/m^2per day given as a 24-hour continuous intravenous infusion for 5 days, starting at the end of the cisplatin infusion. Treatment is repeated every three weeks. Patients must receive premedication with antiemetics and appropriate hydration for cisplatin administration [see Dosage and Administration (2.7)].

2.5 Head and Neck Cancer

Patients must receive premedication with antiemetics, and appropriate hydration (prior to and after cisplatin administration). Prophylaxis for neutropenic infections should be administered. All patients treated on the DOCIVYX containing arms of the TAX323 and TAX324 studies received prophylactic antibiotics.

Induction Chemotherapy Followed by Radiotherapy (TAX323)

For the induction treatment of locally advanced inoperable SCCHN, the recommended dose of DOCIVYX is 75 mg/m^2 as a 1-hour intravenous infusion followed by cisplatin 75 mg/m^2 intravenously over 1 hour, on day one, followed by fluorouracil as a continuous intravenous infusion at 750 mg/m^2 per day for five days. This regimen is administered every 3 weeks for 4 cycles. Following chemotherapy, patients should receive radiotherapy [see Dosage and Administration (2.7)].

Induction Chemotherapy Followed by Chemoradiotherapy (TAX324)

For the induction treatment of patients with locally advanced (unresectable, low surgical cure, or organ preservation) SCCHN, the recommended dose of DOCIVYX is 75 mg/m^2 as a 1-hour intravenous infusion on day 1, followed by cisplatin 100 mg/m^2 administered as a 30-minute to 3 hour infusion, followed by fluorouracil 1000 mg/m^2/day as a continuous infusion from day 1 to day 4. This regimen is administered every 3 weeks for 3 cycles. Following chemotherapy, patients should receive chemoradiotherapy [see Dosage and Administration (2.7)].

2.6 Premedication Regimen

All patients should be premedicated with oral corticosteroids (see below for CRPC) such as dexamethasone 16 mg per day (e.g., 8 mg twice daily) for 3 days starting 1 day prior to DOCIVYX administration in order to reduce the incidence and severity of fluid retention as well as the severity of hypersensitivity reactions [see Boxed Warning, Warnings and Precautions (5.5)].

For metastatic CRPC, given the concurrent use of prednisone, the recommended premedication regimen is oral dexamethasone 8 mg at 12 hours, 3 hours, and 1 hour before the DOCIVYX infusion [see Warnings and Precautions (5.5)].

2.7 Dosage Adjustments during Treatment

Breast Cancer

Patients who are dosed initially at 100 mg/m^2 and who experience either febrile neutropenia, neutrophils <500 cells/mm^3 for more than 1 week, or severe or cumulative cutaneous reactions during DOCIVYX therapy should have the dosage adjusted from 100 mg/m^2 to 75 mg/m^2. If the patient continues to experience these reactions, the dosage should either be decreased from 75 mg/m^2 to 55 mg/m^2 or the treatment should be discontinued. Conversely, patients who are dosed initially at 60 mg/m^2 and who do not experience febrile neutropenia, neutrophils <500 cells/mm^3 for more than 1 week, severe or cumulative cutaneous reactions, or severe peripheral neuropathy during DOCIVYX therapy may tolerate higher doses. Patients who develop ≥grade 3 peripheral neuropathy should have DOCIVYX treatment discontinued entirely.

Combination Therapy with DOCIVYX Injection in the Adjuvant Treatment of Breast Cancer

DOCIVYX in combination with doxorubicin and cyclophosphamide should be administered when the neutrophil count is ≥1,500 cells/mm^3. Patients who experience febrile neutropenia should receive G- CSF in all subsequent cycles. Patients who continue to experience this reaction should remain on G- CSF and have their DOCIVYX dose reduced to 60 mg/m^2. Patients who experience grade 3 or 4 stomatitis should have their DOCIVYX dose decreased to 60 mg/m^2. Patients who experience severe or cumulative cutaneous reactions or moderate neurosensory signs and/or symptoms during DOCIVYX therapy should have their dosage of DOCIVYX reduced from 75 mg/m^2 to 60 mg/m^2. If the patient continues to experience these reactions at 60 mg/m^2, treatment should be discontinued.

Non-small Cell Lung Cancer

Monotherapy with DOCIVYX for NSCLC treatment after failure of prior platinum-based chemotherapy

Patients who are dosed initially at 75 mg/m^2 and who experience either febrile neutropenia, neutrophils <500 cells/mm^3 for more than one week, severe or cumulative cutaneous reactions, or other grade 3/4 non-hematological toxicities during DOCIVYX treatment should have treatment withheld until resolution of the toxicity and then resumed at 55 mg/m^2. Patients who develop ≥grade 3 peripheral neuropathy should have DOCIVYX treatment discontinued entirely.

Combination therapy with DOCIVYX for chemotherapy-naive NSCLC

For patients who are dosed initially at DOCIVYX 75 mg/m^2 in combination with cisplatin, and whose nadir of platelet count during the previous course of therapy is <25,000 cells/mm^3, in patients who experience febrile neutropenia, and in patients with serious non-hematologic toxicities, the DOCIVYX dosage in subsequent cycles should be reduced to 65 mg/m^2. In patients who require a further dose reduction, a dose of 50 mg/m^2 is recommended. For cisplatin dosage adjustments, see manufacturers' prescribing information.

Prostate Cancer

Combination therapy with DOCIVYX for metastatic CRPC

DOCIVYX should be administered when the neutrophil count is ≥1,500 cells/mm^3. Patients who experience either febrile neutropenia, neutrophils <500 cells/mm^3 for more than one week, severe or cumulative cutaneous reactions or moderate neurosensory signs and/or symptoms during DOCIVYX therapy should have the dosage of DOCIVYX reduced from 75 mg/m^2 to 60 mg/m^2. If the patient continues to experience these reactions at 60 mg/m^2, the treatment should be discontinued.

Gastric or Head and Neck Cancer

DOCIVYX in combination with cisplatin and fluorouracil in gastric cancer or head and neck cancer

Patients treated with DOCIVYX in combination with cisplatin and fluorouracil must receive antiemetics and appropriate hydration according to current institutional guidelines. In both studies, G- CSF was recommended during the second and/or subsequent cycles in case of febrile neutropenia, or documented infection with neutropenia, or neutropenia lasting more than 7 days. If an episode of febrile neutropenia, prolonged neutropenia or neutropenic infection occurs despite G-CSF use, the DOCIVYX dose should be reduced from 75 mg/m^2 to 60 mg/m^2. If subsequent episodes of complicated neutropenia occur the DOCIVYX dose should be reduced from 60 mg/m^2 to 45 mg/m^2. In case of grade 4 thrombocytopenia the DOCIVYX dose should be reduced from 75 mg/m^2 to 60 mg/m^2. Do not retreat patients with subsequent cycles of DOCIVYX until neutrophils recover to a level >1,500 cells/mm^3 [see Contraindications (4)]. Avoid retreating patients until platelets recover to a level >100,000 cells/mm^3. Discontinue treatment if these toxicities persist [see Warnings and Precautions (5.3)].

Recommended dose modifications for toxicities in patients treated with DOCIVYX in combination with cisplatin and fluorouracil are shown in Table 1.

Table 1: Recommended Dose Modifications for Toxicities in Patients Treated with DOCIVYX in Combination with Cisplatin and Fluorouracil
Toxicity | Dosage adjustment
Diarrhea grade 3 | First episode: reduce fluorouracil dose by 20%. Second episode: then reduce DOCIVYX dose by 20%.
Diarrhea grade 4 | First episode: reduce DOCIVYX and fluorouracil doses by 20%. Second episode: discontinue treatment.
Stomatitis/mucositis grade 3 | First episode: reduce fluorouracil dose by 20%. Second episode: stop fluorouracil only, at all subsequent cycles. Third episode: reduce DOCIVYX dose by 20%.
Stomatitis/mucositis grade 4 | First episode: stop fluorouracil only, at all subsequent cycles. Second episode: reduce DOCIVYX dose by 20%.

Liver dysfunction: In case of AST/ALT >2.5 to ≤5 × ULN and AP ≤2.5 × ULN, or AST/ALT >1.5 to ≤5 × ULN and AP >2.5 to ≤5 × ULN, DOCIVYX should be reduced by 20%.

In case of AST/ALT >5 × ULN and/or AP >5 × ULN DOCIVYX should be stopped.

The dose modifications for cisplatin and fluorouracil in the gastric cancer study are provided below.

Cisplatin dose modifications and delays

Peripheral neuropathy: A neurological examination should be performed before entry into the study, and then at least every 2 cycles and at the end of treatment. In the case of neurological signs or symptoms, more frequent examinations should be performed and the following dose modifications can be made according to NCI-CTCAE grade:

- Grade 2: Reduce cisplatin dose by 20%.
- Grade 3: Discontinue treatment.

Ototoxicity: In the case of grade 3 toxicity, discontinue treatment.

Nephrotoxicity: In the event of a rise in serum creatinine ≥grade 2 (>1.5 × normal value) despite adequate rehydration, CrCl should be determined before each subsequent cycle and the following dose reductions should be considered (see Table 2).

For other cisplatin dosage adjustments, also refer to the manufacturers' prescribing information.

Table 2: Dose Reductions for Evaluation of Creatinine Clearance
Creatinine clearance results before next cycle | Cisplatin dose next cycle
CrCl ≥60 mL/min | Full dose of cisplatin was given. CrCl was to be repeated before each treatment cycle.
CrCl between 40 and 59 mL/min | Dose of cisplatin was reduced by 50% at subsequent cycle. If CrCl was >60 mL/min at end of cycle, full cisplatin dose was reinstituted at the next cycle. If no recovery was observed, then cisplatin was omitted from the next treatment cycle.
CrCl <40 mL/min | Dose of cisplatin was omitted in that treatment cycle only. If CrCl was still <40 mL/min at the end of cycle, cisplatin was discontinued. If CrCl was >40 and <60 mL/min at end of cycle, a 50% cisplatin dose was given at the next cycle. If CrCl was >60 mL/min at end of cycle, full cisplatin dose was given at next cycle.
CrCl = Creatinine clearance

Fluorouracil dose modifications and treatment delays

For diarrhea and stomatitis, see Table 1.

In the event of grade 2 or greater plantar-palmar toxicity, fluorouracil should be stopped until recovery. The fluorouracil dosage should be reduced by 20%.

For other greater than grade 3 toxicities, except alopecia and anemia, chemotherapy should be delayed (for a maximum of 2 weeks from the planned date of infusion) until resolution to grade ≤1 and then recommenced, if medically appropriate.

For other fluorouracil dosage adjustments, also refer to the manufacturers' prescribing information.

Combination Therapy with Strong CYP3A4 Inhibitors

Avoid using concomitant strong CYP3A4 inhibitors (e.g., ketoconazole, itraconazole, clarithromycin, atazanavir, indinavir, nefazodone, nelfinavir, ritonavir, saquinavir, telithromycin and voriconazole). There are no clinical data with a dose adjustment in patients receiving strong CYP3A4 inhibitors. Based on extrapolation from a pharmacokinetic study with ketoconazole in 7 patients, consider a 50% docetaxel dose reduction if patients require coadministration of a strong CYP3A4 inhibitor [see Drug Interactions (7), Clinical Pharmacology (12.3)].

2.8 Administration Precautions

DOCIVYX is a hazardous anticancer drug and, as with other potentially toxic compounds, caution should be exercised when handling and preparing DOCIVYX solutions. The use of gloves is recommended [see How Supplied/Storage and Handling (16.3)].

If DOCIVYX Injection solution, or final infusion solution should come into contact with the skin, immediately and thoroughly wash with soap and water. If DOCIVYX Injection solution, or final infusion solution should come into contact with mucosa, immediately and thoroughly wash with water.

Contact of the DOCIVYX with plasticized polyvinyl chloride (PVC) equipment or devices used to prepare solutions for infusion is not recommended. In order to minimize patient exposure to the plasticizer DEHP (di-2- ethylhexyl phthalate), which may be leached from PVC infusion bags or sets, the DOCIVYX final infusion solution should be administered through polyethylene-lined administration sets.

DOCIVYX Injection requires NO prior dilution with a diluent and is ready to add to the infusion solution.

Please follow the preparation instructions provided below.

2.9 Preparation and Administration

DOCIVYX Injection (10 mg/mL) requires NO prior dilution with a diluent and is ready to add to the infusion solution. Use only a 21-gauge needle to withdraw DOCIVYX from the vial because larger bore needles (e.g., 18 and 19 gauge) may result in stopper coring and rubber particulates.

1. DOCIVYX vials should be stored between 2°C and 25°C (36°F and 77°F). If the vials are stored under refrigeration, allow the appropriate number of vials of DOCIVYX vials to stand at room temperature for approximately 5 minutes before use.
2. Using only a 21-gauge needle, aseptically withdraw the required amount of DOCIVYX Injection (10 mg docetaxel/mL) with a calibrated syringe and inject via a single injection (one shot) into a 250 mL infusion bag or bottle of either 0.9% Sodium Chloride Injection, USP or 5% Dextrose Injection, USP to produce a final concentration of 0.3 mg/mL to 0.74 mg/mL.
3. If a dose greater than 200 mg of DOCIVYX is required, use a larger volume of the infusion vehicle so that a concentration of 0.74 mg/mL DOCIVYX is not exceeded.
4. Thoroughly mix the infusion by gentle manual rotation.
5. As with all parenteral products, DOCIVYX should be inspected visually for particulate matter or discoloration prior to administration whenever the solution and container permit. If the DOCIVYX final infusion solution is not clear or appears to have precipitation, it should be discarded.
6. DOCIVYX final infusion solution is supersaturated, therefore may crystallize over time. If crystals appear, the solution must no longer be used and shall be discarded.

The DOCIVYX final infusion solution should be administered intravenously as a 1-hour infusion under ambient room temperature (below 25°C) and lighting conditions.

2.10 Stability

DOCIVYX final infusion solution, if stored between 2°C and 25°C (36°F and 77°F), is stable for 6 hours. DOCIVYX final infusion solution (in either 0.9% Sodium Chloride Injection, USP or 5% Dextrose Injection, USP) should be used within 6 hours (including the 1-hour intravenous administration).

In addition, physical and chemical in-use stability of the infusion solution prepared as recommended has been demonstrated in non-PVC bags up to 48 hours when stored between 2°C and 8°C (36°F and 46°F).

3 DOSAGE FORMS AND STRENGTHS

DOCIVYX (docetaxel) Injection, is a sterile, non-pyrogenic, pale-yellow to brownish-yellow solution available in the following strengths: 20 mg/2 mL, 80 mg/8 mL and 160 mg/16 mL in single-dose vials.

4 CONTRAINDICATIONS

DOCIVYX is contraindicated in patients with:

- neutrophil counts of <1500 cells/mm3 [see Warnings and Precautions (5.3)].
- a history of severe hypersensitivity reactions to docetaxel. Severe reactions, including anaphylaxis, have occurred [see Warnings and Precautions (5.5)].

5 WARNINGS AND PRECAUTIONS

5.1 Toxic Deaths

Breast Cancer

DOCIVYX administered at 100 mg/m^2 was associated with deaths considered possibly or probably related to treatment in 2.0% (19/965) of metastatic breast cancer patients, both previously treated and untreated, with normal baseline liver function and in 11.5% (7/61) of patients with various tumor types who had abnormal baseline liver function (AST and/or ALT >1.5 times ULN together with AP >2.5 times ULN). Among patients dosed at 60 mg/m^2, mortality related to treatment occurred in 0.6% (3/481) of patients with normal liver function, and in 3 of 7 patients with abnormal liver function. Approximately half of these deaths occurred during the first cycle. Sepsis accounted for the majority of the deaths.

Non-small Cell Lung Cancer

DOCIVYX administered at a dose of 100 mg/m^2 in patients with locally advanced or metastatic non-small cell lung cancer who had a history of prior platinum-based chemotherapy was associated with increased treatment-related mortality (14% and 5% in two randomized, controlled studies). There were 2.8% treatment-related deaths among the 176 patients treated at the 75 mg/m^2 dose in the randomized trials. Among patients who experienced treatment-related mortality at the 75 mg/m^2 dose level, 3 of 5 patients had an ECOG PS of 2 at study entry [see Dosage and Administration (2.2), Clinical Studies (14)].

5.2 Hepatic Impairment

Patients with elevations of bilirubin or abnormalities of transaminase concurrent with alkaline phosphatase are at increased risk for the development of severe neutropenia, febrile neutropenia, infections, severe thrombocytopenia, severe stomatitis, severe skin toxicity, and toxic death.

Avoid DOCIVYX in patients with bilirubin > upper limit of normal (ULN), or to patients with AST and/or ALT >1.5 × ULN concomitant with alkaline phosphatase >2.5 × ULN [see Warnings and Precautions (5.1)].

For patients with isolated elevations of transaminase >1.5 × ULN, consider DOCIVYX dose modifications [see Dosage and Administration (2.7)].

Measure bilirubin, AST or ALT, and alkaline phosphatase prior to each cycle of DOCIVYX therapy.

5.3 Hematologic Effects

Perform frequent peripheral blood cell counts on all patients receiving DOCIVYX. Do not retreat patients with subsequent cycles of DOCIVYX until neutrophils recover to a level >1500 cells/mm^3 [see Contraindications (4)]. Avoid retreating patients until platelets recover to a level >100,000 cells/mm^3.

A 25% reduction in the dose of DOCIVYX is recommended during subsequent cycles following severe neutropenia (<500 cells/mm^3) lasting 7 days or more, febrile neutropenia, or a grade 4 infection in a DOCIVYX cycle [see Dosage and Administration (2.7)].

Neutropenia (<2000 neutrophils/mm^3) occurs in virtually all patients given 60 mg/m^2 to 100 mg/m^2 of DOCIVYX and grade 4 neutropenia (<500 cells/mm^3) occurs in 85% of patients given 100 mg/m^2 and 75% of patients given 60 mg/m^2. Frequent monitoring of blood counts is, therefore, essential so that dose can be adjusted. DOCIVYX should not be administered to patients with neutrophils <1500 cells/mm^3.

Febrile neutropenia occurred in about 12% of patients given 100 mg/m^2 but was very uncommon in patients given 60 mg/m^2. Hematologic responses, febrile reactions and infections, and rates of septic death for different regimens are dose related [see Adverse Reactions (6.1), Clinical Studies (14)].

Three breast cancer patients with severe liver impairment (bilirubin >1.7 times ULN) developed fatal gastrointestinal bleeding associated with severe drug-induced thrombocytopenia. In gastric cancer patients treated with docetaxel in combination with cisplatin and fluorouracil (TCF), febrile neutropenia and/or neutropenic infection occurred in 12% of patients receiving G-CSF compared to 28% who did not. Patients receiving TCF should be closely monitored during the first and subsequent cycles for febrile neutropenia and neutropenic infection [see Dosage and Administration (2.7), Adverse Reactions (6)].

5.4 Enterocolitis and Neutropenic Colitis

Enterocolitis and neutropenic colitis (typhlitis) have occurred in patients treated with DOCIVYX alone and in combination with other chemotherapeutic agents, despite the coadministration of G-CSF. Caution is recommended for patients with neutropenia, particularly at risk for developing gastrointestinal complications. Enterocolitis and neutropenic enterocolitis may develop at any time, and could lead to death as early as the first day of symptom onset. Monitor patients closely from onset of any symptoms of gastrointestinal toxicity. Inform patients to contact their healthcare provider with new, or worsening symptoms of gastrointestinal toxicity [see Dosage and Administration (2), Warnings and Precautions (5.3), Adverse Reactions (6.2)].

5.5 Hypersensitivity Reactions

Monitor patients closely for hypersensitivity reactions, especially during the first and second infusions. Severe hypersensitivity reactions characterized by generalized rash/erythema, hypotension and/or bronchospasm, or fatal anaphylaxis, have been reported in patients premedicated with 3 days of corticosteroids. Severe hypersensitivity reactions require immediate discontinuation of the DOCIVYX infusion and aggressive therapy. Do not rechallenge patients with a history of severe hypersensitivity reactions with DOCIVYX [see Contraindications (4)].

Patients who have previously experienced a hypersensitivity reaction to paclitaxel may develop a hypersensitivity reaction to docetaxel that may include severe or fatal reactions such as anaphylaxis. Monitor patients with a previous history of hypersensitivity to paclitaxel closely during initiation of DOCIVYX therapy. Hypersensitivity reactions may occur within a few minutes following initiation of a DOCIVYX infusion. If minor reactions such as flushing or localized skin reactions occur, interruption of therapy is not required. All patients should be premedicated with an oral corticosteroid prior to the initiation of the infusion of DOCIVYX [see Dosage and Administration (2.6)].

5.6 Fluid Retention

Severe fluid retention has been reported following DOCIVYX therapy. Patients should be premedicated with oral corticosteroids prior to each DOCIVYX administration to reduce the incidence and severity of fluid retention [see Dosage and Administration (2.6)]. Patients with pre-existing effusions should be closely monitored from the first dose for the possible exacerbation of the effusions.

When fluid retention occurs, peripheral edema usually starts in the lower extremities and may become generalized with a median weight gain of 2 kg.

Among 92 breast cancer patients premedicated with 3-day corticosteroids, moderate fluid retention occurred in 27.2% and severe fluid retention in 6.5%. The median cumulative dose to onset of moderate or severe fluid retention was 819 mg/m^2. Nine of 92 patients (9.8%) of patients discontinued treatment due to fluid retention: 4 patients discontinued with severe fluid retention; the remaining 5 had mild or moderate fluid retention. The median cumulative dose to treatment discontinuation due to fluid retention was 1021 mg/m^2. Fluid retention was completely, but sometimes slowly, reversible with a median of 16 weeks from the last infusion of DOCIVYX to resolution (range: 0 to 42+ weeks). Patients developing peripheral edema may be treated with standard measures, e.g., salt restriction, oral diuretic(s).

5.7 Second Primary Malignancies

Second primary malignancies, notably acute myeloid leukemia (AML), myelodysplastic syndrome (MDS), non-Hodgkin's lymphoma (NHL), and renal cancer, have been reported in patients treated with docetaxel-containing regimens. These adverse reactions may occur several months or years after docetaxel-containing therapy.

Treatment-related AML or MDS has occurred in patients given anthracyclines and/or cyclophosphamide, including use in adjuvant therapy for breast cancer. In the adjuvant breast cancer trial (TAX316) AML occurred in 3 of 744 patients who received DOCIVYX, doxorubicin and cyclophosphamide (TAC) and in 1 of 736 patients who received fluorouracil, doxorubicin, and cyclophosphamide [see Clinical Studies (14.2)]. In TAC-treated patients, the risk of delayed myelodysplasia or myeloid leukemia requires hematological follow-up. Monitor patients for second primary malignancies [see Adverse Reactions (6.1)].

5.8 Cutaneous Reactions

Localized erythema of the extremities with edema followed by desquamation has been observed. In case of severe skin toxicity, an adjustment in dosage is recommended [see Dosage and Administration (2.7)]. The discontinuation rate due to skin toxicity was 1.6% (15/965) for metastatic breast cancer patients. Among 92 breast cancer patients premedicated with 3-day corticosteroids, there were no cases of severe skin toxicity reported and no patient discontinued DOCIVYX due to skin toxicity.

Severe cutaneous adverse reactions (SCARs) such as Stevens-Johnson syndrome (SJS), toxic epidermal necrolysis (TEN), and acute generalized exanthematous pustulosis (AGEP) have been reported in association with docetaxel treatment. Patients should be informed about the signs and symptoms of serious skin manifestations and monitored closely. Permanent treatment discontinuation should be considered in patients who experience SCARs.

5.9 Neurologic Reactions

Severe neurosensory symptoms (e.g., paresthesia, dysesthesia, pain) were observed in 5.5% (53/965) of metastatic breast cancer patients, and resulted in treatment discontinuation in 6.1%. When these symptoms occur, dosage must be adjusted. If symptoms persist, treatment should be discontinued [see Dosage and Administration (2.7)]. Patients who experienced neurotoxicity in clinical trials and for whom follow-up information on the complete resolution of the event was available had spontaneous reversal of symptoms with a median of 9 weeks from onset (range: 0 to 106 weeks). Severe peripheral motor neuropathy mainly manifested as distal extremity weakness occurred in 4.4% (42/965).

5.10 Eye Disorders

Cystoid macular edema (CME) has been reported in patients treated with DOCIVYX. Patients with impaired vision should undergo a prompt and comprehensive ophthalmologic examination. If CME is diagnosed, DOCIVYX treatment should be discontinued and appropriate treatment initiated. Alternative non-taxane cancer treatment should be considered.

5.11 Asthenia

Severe asthenia has been reported in 14.9% (144/965) of metastatic breast cancer patients but has led to treatment discontinuation in only 1.8%. Symptoms of fatigue and weakness may last a few days up to several weeks and may be associated with deterioration of performance status in patients with progressive disease.

5.12 Embryo-Fetal Toxicity

Based on findings from animal reproduction studies and its mechanism of action, DOCIVYX can cause fetal harm when administered to a pregnant woman [see Clinical Pharmacology (12.1)]. Available data from case reports in the literature and pharmacovigilance with docetaxel use in pregnant women are not sufficient to inform the drug-associated risk of major birth defects, miscarriage or adverse maternal or fetal outcomes. In animal reproduction studies, administration of docetaxel to pregnant rats and rabbits during the period of organogenesis caused embryo-fetal toxicities, including intrauterine mortality, at doses as low as 0.02 and 0.003 times the recommended human dose based on body surface area, respectively.

Advise pregnant women and females of reproductive potential of the potential risk to a fetus. Verify pregnancy status in females of reproductive potential prior to initiating DOCIVYX. Advise females of reproductive potential to use effective contraception during treatment and for 2 months after the last dose of DOCIVYX. Advise male patients with female partners of reproductive potential to use effective contraception during treatment and for 4 months after the last dose of DOCIVYX [see Use in Specific Populations (8.1, 8.3)].

5.13 Alcohol Content

Cases of intoxication have been reported with some formulations of docetaxel due to the alcohol content. The alcohol content in a dose of DOCIVYX may affect the central nervous system and should be taken into account for patients in whom alcohol intake should be avoided or minimized. Consideration should be given to the alcohol content in DOCIVYX on the ability to drive or use machines immediately after the infusion. Each administration of DOCIVYX at 100 mg/m^2 delivers 2.0 g/m^2 of ethanol. For a patient with a BSA of 2.0 m^2, this would deliver 4.0 grams of ethanol [see Description (11)]. Other docetaxel products may have a different amount of alcohol.

5.14 Tumor Lysis Syndrome

Tumor lysis syndrome has been reported with docetaxel [see Adverse Reactions (6.2)]. Patients at risk of tumor lysis syndrome (e.g., with renal impairment, hyperuricemia, bulky tumor) should be closely monitored prior to initiating DOCIVYX and periodically during treatment. Correction of dehydration and treatment of high uric acid levels are recommended prior to initiation of treatment.

6 ADVERSE REACTIONS

The most serious adverse reactions from DOCIVYX are:

- Toxic Deaths [see Boxed Warning, Warnings and Precautions (5.1)]
- Hepatic Impairment [see Boxed Warning, Warnings and Precautions (5.2)]
- Hematologic Effects [see Boxed Warning, Warnings and Precautions (5.3)]
- Enterocolitis and Neutropenic Colitis [see Warnings and Precautions (5.4)]
- Hypersensitivity Reactions [see Boxed Warning, Warnings and Precautions (5.5)]
- Fluid Retention [see Boxed Warning, Warnings and Precautions (5.6)]
- Second Primary Malignancies [see Warnings and Precautions (5.7)]
- Cutaneous Reactions [see Warnings and Precautions (5.8)]
- Neurologic Reactions [see Warnings and Precautions (5.9)]
- Eye Disorders [see Warnings and Precautions (5.10)]
- Asthenia [see Warnings and Precautions (5.11)]
- Alcohol Content [see Warnings and Precautions (5.13)]

The most common adverse reactions across all DOCIVYX indications are infections, neutropenia, anemia, febrile neutropenia, hypersensitivity, thrombocytopenia, neuropathy, dysgeusia, dyspnea, constipation, anorexia, nail disorders, fluid retention, asthenia, pain, nausea, diarrhea, vomiting, mucositis, alopecia, skin reactions, and myalgia. Incidence varies depending on the indication.

Adverse reactions are described according to indication. Because clinical trials are conducted under widely varying conditions, adverse reaction rates observed in the clinical trials of a drug cannot be directly compared to rates in the clinical trials of another drug and may not reflect the rates observed in practice.

Responding patients may not experience an improvement in performance status on therapy and may experience worsening. The relationship between changes in performance status, response to therapy, and treatment-related side effects has not been established.

6.1 Clinical Trials Experience

Breast Cancer

Monotherapy with DOCIVYX for locally advanced or metastatic breast cancer after failure of prior chemotherapy

DOCIVYX 100 mg/m^2: Adverse drug reactions occurring in at least 5% of patients are compared for three populations who received DOCIVYX administered at 100 mg/m^2 as a 1-hour infusion every 3 weeks: 2045 patients with various tumor types and normal baseline liver function tests; the subset of 965 patients with locally advanced or metastatic breast cancer, both previously treated and untreated with chemotherapy, who had normal baseline liver function tests; and an additional 61 patients with various tumor types who had abnormal liver function tests at baseline. These reactions were described using COSTART terms and were considered possibly or probably related to DOCIVYX. At least 95% of these patients did not receive hematopoietic support. The safety profile is generally similar in patients receiving DOCIVYX for the treatment of breast cancer and in patients with other tumor types. (See Table 3.)

Table 3: Summary of Adverse Reactions in Patients Receiving DOCIVYX at 100 mg/m^2
Adverse Reaction | All Tumor Types Normal LFTs* n=2045 % | All Tumor Types Elevated LFTs † n=61 % | Breast Cancer Normal LFTs * n=965 %
Hematologic
Neutropenia
<2000 cells/mm3 | 96 | 96 | 99
<500 cells/mm3 | 75 | 88 | 86
Leukopenia
<4000 cells/mm3 | 96 | 98 | 99
<1000 cells/mm3 | 32 | 47 | 44
Thrombocytopenia
<100,000 cells/mm3 | 8 | 25 | 9
Anemia
<11 g/dL | 90 | 92 | 94
<8 g/dL | 9 | 31 | 8
Febrile Neutropenia‡ | 11 | 26 | 12
Septic Death | 2 | 5 | 1
Non-Septic Death | 1 | 7 | 1
Infections Any Severe | 22 6 | 33 16 | 22 6
Fever in Absence of Infection Any Severe | 31 2 | 41 8 | 35 2
Hypersensitivity
Reactions
Regardless of
Premedication
Any | 21 | 20 | 18
Severe | 4 | 10 | 3
With 3-day Premedication | n=92 | n=3 | n=92
Any | 15 | 33 | 15
Severe | 2 | 0 | 2
Fluid Retention
Regardless of
Premedication
Any | 47 | 39 | 60
Severe | 7 | 8 | 9
With 3-day Premedication | n=92 | n=3 | n=92
Any | 64 | 67 | 64
Severe | 7 | 33 | 7
Neurosensory Any Severe | 49 4 | 34 0 | 58 6
Cutaneous Any Severe | 48 5 | 54 10 | 47 5
Nail Changes Any Severe | 31 3 | 23 5 | 41 4
Gastrointestinal Nausea Vomiting Diarrhea Severe | 39 22 39 5 | 38 23 33 5 | 42 23 43 6
Stomatitis Any Severe | 42 6 | 49 13 | 52 7
Alopecia | 76 | 62 | 74
Asthenia Any Severe | 62 13 | 53 25 | 66 15
Myalgia Any Severe | 19 2 | 16 2 | 21 2
Arthralgia | 9 | 7 | 8
Infusion Site Reactions | 4 | 3 | 4
* Normal Baseline LFTs: Transaminases ≤1.5 times ULN or alkaline phosphatase ≤2.5 times ULN or isolated elevations of transaminases or alkaline phosphatase up to 5 times ULN
† Elevated Baseline LFTs: AST and/or ALT >1.5 times ULN concurrent with alkaline phosphatase >2.5 times ULN
‡ Febrile Neutropenia: ANC grade 4 with fever >38°C with intravenous antibiotics and/or hospitalization

Hematologic reactions

Reversible marrow suppression was the major dose-limiting toxicity of DOCIVYX [see Warnings and Precautions (5.3)]. The median time to nadir was 7 days, while the median duration of severe neutropenia (<500 cells/mm^3) was 7 days. Among 2045 patients with solid tumors and normal baseline LFTs, severe neutropenia occurred in 75.4% and lasted for more than 7 days in 2.9% of cycles.

Febrile neutropenia (<500 cells/mm^3 with fever >38°C with intravenous antibiotics and/or hospitalization) occurred in 11% of patients with solid tumors, in 12.3% of patients with metastatic breast cancer, and in 9.8% of 92 breast cancer patients premedicated with 3-day corticosteroids.

Severe infectious episodes occurred in 6.1% of patients with solid tumors, in 6.4% of patients with metastatic breast cancer, and in 5.4% of 92 breast cancer patients premedicated with 3-day corticosteroids.

Thrombocytopenia (<100,000 cells/mm^3) associated with fatal gastrointestinal hemorrhage has been reported.

Hypersensitivity reactions

Severe hypersensitivity reactions have been reported [see Boxed Warning, Warnings and Precautions (5.5)]. Minor events, including flushing, rash with or without pruritus, chest tightness, back pain, dyspnea, drug fever, or chills, have been reported and resolved after discontinuing the infusion and instituting appropriate therapy.

Fluid retention

Fluid retention can occur with the use of DOCIVYX [see Boxed Warning, Dosage and Administration (2.6), Warnings and Precautions (5.6)].

Cutaneous reactions

Severe skin toxicity is discussed elsewhere in the label [see Warnings and Precautions (5.8)]. Reversible cutaneous reactions characterized by a rash including localized eruptions, mainly on the feet and/or hands, but also on the arms, face, or thorax, usually associated with pruritus, have been observed. Eruptions generally occurred within 1 week after DOCIVYX infusion, recovered before the next infusion, and were not disabling.

Severe nail disorders were characterized by hypo or hyperpigmentation, and occasionally by onycholysis (in 0.8% of patients with solid tumors) and pain.

Neurologic reactions

Neurologic reactions are discussed elsewhere in the label [see Warnings and Precautions (5.9)].

Gastrointestinal reactions

Nausea, vomiting, and diarrhea were generally mild to moderate. Severe reactions occurred in 3%–5% of patients with solid tumors and to a similar extent among metastatic breast cancer patients. The incidence of severe reactions was 1% or less for the 92 breast cancer patients premedicated with 3-day corticosteroids.

Severe stomatitis occurred in 5.5% of patients with solid tumors, in 7.4% of patients with metastatic breast cancer, and in 1.1% of the 92 breast cancer patients premedicated with 3-day corticosteroids.

Cardiovascular reactions

Hypotension occurred in 2.8% of patients with solid tumors; 1.2% required treatment. Clinically meaningful events such as heart failure, sinus tachycardia, atrial flutter, dysrhythmia, unstable angina, pulmonary edema, and hypertension have occurred. Seven of 86 (8.1%) of metastatic breast cancer patients receiving DOCIVYX 100 mg/m^2 in a randomized trial and who had serial left ventricular ejection fractions assessed developed deterioration of LVEF by ≥10% associated with a drop below the institutional lower limit of normal.

Infusion site reactions

Infusion site reactions were generally mild and consisted of hyperpigmentation, inflammation, redness or dryness of the skin, phlebitis, extravasation, or swelling of the vein.

Hepatic reactions

In patients with normal LFTs at baseline, bilirubin values greater than the ULN occurred in 8.9% of patients. Increases in AST or ALT >1.5 times the ULN, or alkaline phosphatase >2.5 times ULN, were observed in 18.9% and 7.3% of patients, respectively. While on DOCIVYX, increases in AST and/or ALT >1.5 times ULN concomitant with alkaline phosphatase >2.5 times ULN occurred in 4.3% of patients with normal LFTs at baseline. Whether these changes were related to the drug or underlying disease has not been established.

Hematologic and other toxicity: Relation to dose and baseline liver chemistry abnormalities

Hematologic and other toxicity is increased at higher doses and in patients with elevated baseline liver function tests (LFTs). In the following tables, adverse drug reactions are compared for three populations: 730 patients with normal LFTs given DOCIVYX at 100 mg/m^2 in the randomized and single arm studies of metastatic breast cancer after failure of previous chemotherapy; 18 patients in these studies who had abnormal baseline LFTs (defined as AST and/or ALT >1.5 times ULN concurrent with alkaline phosphatase >2.5 times ULN); and 174 patients in Japanese studies given DOCIVYX at 60 mg/m^2 who had normal LFTs (see Tables 4 and 5).

Table 4: Hematologic Adverse Reactions in Breast Cancer Patients Previously Treated with Chemotherapy Treated at DOCIVYX 100 mg/m^2 with Normal or Elevated Liver Function Tests or 60 mg/m^2 with Normal Liver Function Tests
Adverse Reaction | DOCIVYX 100 mg/m 2 |  | DOCIVYX 60 mg/m 2
Adverse Reaction | Norm al L FTs * n=730 % | Elevate d L FTs † n=18 % | Normal LFTs * n=174 %
Neutropenia
Any <2000 cells/mm^3 | 98 | 100 | 95
Grade 4 <500 cells/mm^3 | 84 | 94 | 75
T hrombocytopenia Any <100,000 cells/mm^3 | 11 | 44 | 14
Grade 4 <20,000 cells/mm3 | 1 | 17 | 1
Anemia <11 g/dL | 95 | 94 | 65
Infection ‡ Any Grade 3 and 4 | 23 7 | 39 33 | 1 0
Febrile Neutropenia § By Patient By Course | 12 2 | 33 9 | 0 0
Septic Death | 2 | 6 | 1
Non-Septic Death | 1 | 11 | 0
* Normal Baseline LFTs: Transaminases ≤1.5 times ULN or alkaline phosphatase ≤2.5 times ULN or isolated elevations of transaminases or alkaline phosphatase up to 5 times ULN
† Elevated Baseline LFTs: AST and/or ALT >1.5 times ULN concurrent with alkaline phosphatase >2.5 times ULN
‡ Incidence of infection requiring hospitalization and/or intravenous antibiotics was 8.5% (n=62) among the 730 patients with normal LFTs at baseline; 7 patients had concurrent grade 3 neutropenia, and 46 patients had grade 4 neutropenia.
§ Febrile Neutropenia: For 100 mg/m^2, ANC grade 4 and fever >38°C with intravenous antibiotics and/or hospitalization; for 60 mg/m^2, ANC grade 3/4 and fever >38.1°C

Table 5: Non-hematologic Adverse Reactions in Breast Cancer Patients Previously Treated with Chemotherapy Treated at DOCIVYX 100 mg/m^2 with Normal or Elevated Liver Function Tests or 60 mg/m^2 with Normal Liver Function Tests
Adverse Reaction | DOCIVYX 100 mg/m^2 |  | DOCIVYX 60 mg/m^2
Adverse Reaction | Normal LFTs * n=730 % | Elevat ed L FTs † n=18 % | Normal LFTs * n=174 %
Acute Hypersensitivity Reaction Regardless of Premedication Any Severe | 13 1 | 6 0 | 1 0
Fluid Retention ‡ Regardless of Premedication Any Severe | 56 8 | 61 17 | 13 0
Neurosensory Any Severe | 57 6 | 50 0 | 20 0
Myalgia | 23 | 33 | 3
Cutaneous Any Severe | 45 5 | 61 17 | 31 0
Asthenia Any Severe | 65 17 | 44 22 | 66 0
Diarrhea Any Severe | 42 6 | 28 11 | NA
Stomatitis Any Severe | 53 8 | 67 39 | 19 1
* Normal Baseline LFTs: Transaminases ≤1.5 times ULN or alkaline phosphatase ≤2.5 times ULN or isolated elevations of transaminases or alkaline phosphatase up to 5 times ULN
† Elevated Baseline Liver Function: AST and/or ALT >1.5 times ULN concurrent with alkaline phosphatase >2.5 times ULN
‡ Fluid Retention includes (by COSTART): edema (peripheral, localized, generalized, lymphedema, pulmonary edema, and edema otherwise not specified) and effusion (pleural, pericardial, and ascites); no premedication given with the 60 mg/m^2 dose
NA = not available

In the three-arm monotherapy trial, TAX313, which compared DOCIVYX 60 mg/m^2, 75 mg/m^2 and 100 mg/m^2 in advanced breast cancer, grade 3/4 or severe adverse reactions occurred in 49.0% of patients treated with DOCIVYX 60 mg/m^2 compared to 55.3% and 65.9% treated with 75 mg/m^2 and 100 mg/m^2, respectively. Discontinuation due to adverse reactions was reported in 5.3% of patients treated with 60 mg/m^2 versus 6.9% and 16.5% for patients treated at 75 and 100 mg/m^2, respectively. Deaths within 30 days of last treatment occurred in 4.0% of patients treated with 60 mg/m^2 compared to 5.3% and 1.6% for patients treated at 75 mg/m^2 and 100 mg/m^2, respectively.

The following adverse reactions were associated with increasing docetaxel doses: fluid retention (26%, 38%, and 46% at 60 mg/m^2, 75 mg/m^2, and 100 mg/m^2, respectively), thrombocytopenia (7%, 11% and 12%, respectively), neutropenia (92%, 94%, and 97% respectively), febrile neutropenia (5%, 7%, and 14%, respectively), treatment-related grade 3/4 infection (2%, 3%, and 7%, respectively) and anemia (87%, 94%, and 97%, respectively).

Combination therapy with DOCIVYX in the adjuvant treatment of breast cancer

The following table presents treatment-emergent adverse reactions observed in 744 patients, who were treated with DOCIVYX 75 mg/m^2 every 3 weeks in combination with doxorubicin and cyclophosphamide (see Table 6).

Table 6: Clinically Important Treatment-Emergent Adverse Reactions Regardless of Causal Relationship in Patients Receiving DOCIVYX in Combination with Doxorubicin and Cyclophosphamide (TAX316)
 | DOCIVYX 75 mg/m^2 + Doxorubicin 50 mg/m^2 + Cyclophosphami de 50 0 mg/m^2 (TAC) n=744 % |  | Fluorouracil 500 mg/m^2 + Doxorubicin 50 mg/m^2 + Cyclophosphamide 500 mg/m^2 (FAC) n=736 %
Adverse Reaction | Any | Grade 3/4 | Any | Grade 3/4
Anemia | 92 | 4 | 72 | 2
Neutropenia | 71 | 66 | 82 | 49
Fever in absence of infection | 47 | 1 | 17 | 0
Infection | 39 | 4 | 36 | 2
Thrombocytopenia | 39 | 2 | 28 | 1
Febrile neutropenia | 25 | N/A | 3 | N/A
Neutropenic infection | 12 | N/A | 6 | N/A
Hypersensitivity reactions | 13 | 1 | 4 | 0
Lymphedema | 4 | 0 | 1 | 0
Fluid Retention * Peripheral edema Weight gain | 35 27 13 | 1 0 0 | 15 7 9 | 0 0 0
Neuropathy sensory | 26 | 0 | 10 | 0
Neuro-cortical | 5 | 1 | 6 | 1
Neuropathy motor | 4 | 0 | 2 | 0
Neuro-cerebellar | 2 | 0 | 2 | 0
Syncope | 2 | 1 | 1 | 0
Alopecia | 98 | N/A | 97 | N/A
Skin toxicity | 27 | 1 | 18 | 0
Nail disorders | 19 | 0 | 14 | 0
Nausea | 81 | 5 | 88 | 10
Stomatitis | 69 | 7 | 53 | 2
Vomiting | 45 | 4 | 59 | 7
Diarrhea | 35 | 4 | 28 | 2
Constipation | 34 | 1 | 32 | 1
Taste perversion | 28 | 1 | 15 | 0
Anorexia | 22 | 2 | 18 | 1
Abdominal Pain | 11 | 1 | 5 | 0
Amenorrhea | 62 | N/A | 52 | N/A
Cough | 14 | 0 | 10 | 0
Cardiac dysrhythmias | 8 | 0 | 6 | 0
Vasodilatation | 27 | 1 | 21 | 1
Hypotension | 2 | 0 | 1 | 0
Phlebitis | 1 | 0 | 1 | 0
Asthenia | 81 | 11 | 71 | 6
Myalgia | 27 | 1 | 10 | 0
Arthralgia | 19 | 1 | 9 | 0
Lacrimation disorder | 11 | 0 | 7 | 0
Conjunctivitis | 5 | 0 | 7 | 0
* COSTART term and grading system for events related to treatment.

Of the 744 patients treated with TAC, 36.3% experienced severe treatment-emergent adverse reactions compared to 26.6% of the 736 patients treated with FAC. Dose reductions due to hematologic toxicity occurred in 1% of cycles in the TAC arm versus 0.1% of cycles in the FAC arm. Six percent of patients treated with TAC discontinued treatment due to adverse reactions, compared to 1.1% treated with FAC; fever in the absence of infection and allergy being the most common reasons for withdrawal among TAC-treated patients. Two patients died in each arm within 30 days of their last study treatment; 1 death per arm was attributed to study drugs.

Fever and infection

During the treatment period, fever in the absence of infection was seen in 46.5% of TAC-treated patients and in 17.1% of FAC-treated patients. Grade 3/4 fever in the absence of infection was seen in 1.3% and 0% of TAC and FAC-treated patients, respectively. Infection was seen in 39.4% of TAC- treated patients compared to 36.3% of FAC-treated patients. Grade 3/4 infection was seen in 3.9% and 2.2% of TAC-treated and FAC-treated patients, respectively. There were no septic deaths in either treatment arm during the treatment period.

Gastrointestinal reactions

In addition to gastrointestinal reactions reflected in the table above, 7 patients in the TAC arm were reported to have colitis/enteritis/large intestine perforation versus one patient in the FAC arm. Five of the 7 TAC-treated patients required treatment discontinuation; no deaths due to these events occurred during the treatment period.

Cardiovascular reactions

More cardiovascular reactions were reported in the TAC arm versus the FAC arm during the treatment period: arrhythmias, all grades (6.2% vs 4.9%), and hypotension, all grades (1.9% vs 0.8%). Twenty-six (26) patients (3.5%) in the TAC arm and 17 patients (2.3%) in the FAC arm developed CHF during the study period. All except one patient in each arm were diagnosed with CHF during the follow-up period. Two (2) patients in TAC arm and 4 patients in FAC arm died due to CHF. The risk of CHF was higher in the TAC arm in the first year, and then was similar in both treatment arms.

Adverse reactions during the follow-up period (median follow-up time of 8 years)

In study TAX316, the most common adverse reactions that started during the treatment period and persisted into the follow-up period in TAC and FAC patients are described below (median follow-up time of 8 years).

Nervous system disorders

In study TAX316, peripheral sensory neuropathy started during the treatment period and persisted into the follow-up period in 84 patients (11.3%) in TAC arm and 15 patients (2%) in FAC arm. At the end of the follow-up period (median follow-up time of 8 years), peripheral sensory neuropathy was observed to be ongoing in 10 patients (1.3%) in TAC arm, and in 2 patients (0.3%) in FAC arm.

Skin and subcutaneous tissue disorders

In study TAX316, alopecia persisting into the follow-up period after the end of chemotherapy was reported in 687 of 744 TAC patients (92.3%) and 645 of 736 FAC patients (87.6%). At the end of the follow-up period (actual median follow-up time of 8 years), alopecia was observed to be ongoing in 29 TAC patients (3.9%) and 16 FAC patients (2.2%).

Reproductive system and breast disorders

In study TAX316, amenorrhea that started during the treatment period and persisted into the follow-up period after the end of chemotherapy was reported in 202 of 744 TAC patients (27.2%) and 125 of 736 FAC patients (17.0%). Amenorrhea was observed to be ongoing at the end of the follow-up period (median follow-up time of 8 years) in 121 of 744 TAC patients (16.3%) and 86 FAC patients (11.7%).

General disorders and administration site conditions

In study TAX316, peripheral edema that started during the treatment period and persisted into the follow-up period after the end of chemotherapy was observed in 119 of 744 TAC patients (16.0%) and 23 of 736 FAC patients (3.1%). At the end of the follow-up period (actual median follow-up time of 8 years), peripheral edema was ongoing in 19 TAC patients (2.6%) and 4 FAC patients (0.5%).

In study TAX316, lymphedema that started during the treatment period and persisted into the follow-up period after the end of chemotherapy was reported in 11 of 744 TAC patients (1.5%) and 1 of 736 FAC patients (0.1%). At the end of the follow-up period (actual median follow-up time of 8 years), lymphedema was observed to be ongoing in 6 TAC patients (0.8%) and 1 FAC patient (0.1%).

In study TAX316, asthenia that started during the treatment period and persisted into the follow-up period after the end of chemotherapy was reported in 236 of 744 TAC patients (31.7%) and 180 of 736 FAC patients (24.5%). At the end of the follow-up period (actual median follow-up time of 8 years), asthenia was observed to be ongoing in 29 TAC patients (3.9%) and 16 FAC patients (2.2%).

Acute myeloid leukemia (AML)/Myelodysplastic syndrome (MDS)

AML occurred in the adjuvant breast cancer trial (TAX316). The cumulative risk of developing treatment-related AML at median follow-up time of 8 years in TAX316 was 0.4% for TAC-treated patients and 0.1% for FAC-treated patients. One TAC patient (0.1%) and 1 FAC patient (0.1%) died due to AML during the follow-up period (median follow-up time of 8 years). Myelodysplastic syndrome occurred in 2 of 744 (0.3%) patients who received TAC and in 1 of 736 (0.1%) patients who received FAC. AML occurs at a higher frequency when these agents are given in combination with radiation therapy.

Lung Cancer

Monotherapy with DOCIVYX for unresectable, locally advanced or metastatic NSCLC previously treated with platinum-based chemotherapy

DOCIVYX 75 mg/m^2: Treatment-emergent adverse drug reactions are shown in Table 7. Included in this table are safety data for a total of 176 patients with non-small cell lung carcinoma and a history of prior treatment with platinum-based chemotherapy who were treated in two randomized, controlled trials. These reactions were described using NCI Common Toxicity Criteria regardless of relationship to study treatment, except for the hematologic toxicities or where otherwise noted.

Table 7: Treatment-Emergent Adverse Reactions Regardless of Relationship to Treatment in Patients Receiving DOCIVYX as Monotherapy for Non-small Cell Lung Cancer Previously Treated with Platinum-Based Chemotherapy*
Adverse Reaction | DOCIVYX 75 mg/m 2 n=176 % | Best Supportive Care n=49 % | Vinorelbine/ Ifosfamide n=119 %
Neutropenia Any Grade 3/4 | 84 65 | 14 12 | 83 57
Leukopenia Any Grade 3/4 | 84 49 | 6 0 | 89 43
Thrombocytopenia Any Grade 3/4 | 8 3 | 0 0 | 8 2
Anemia Any Grade 3/4 | 91 9 | 55 12 | 91 14
Febrile Neutropenia † | 6 | NA‡ | 1
Infection Any | 34 | 29 | 30
Grade 3/4 | 10 | 6 | 9
Treatment Related Mortality | 3 | NA‡ | 3
Hypersensitivity Reactions Any Grade 3/4 | 6 3 | 0 0 | 1 0
Fluid Retention Any Severe | 34 3 | ND§ | 23 3
Neurosensory Any Grade 3/4 | 23 2 | 14 6 | 29 5
Neuromotor Any Grade 3/4 | 16 5 | 8 6 | 10 3
Skin Any Grade 3/4 | 20 1 | 6 2 | 17 1
Gastrointestinal Nausea Any Grade 3/4 Vomiting Any Grade 3/4 Diarrhea Any Grade 3/4 | 34 5 22 3 23 3 | 31 4 27 2 6 0 | 31 8 22 6 12 4
Alopecia | 56 | 35 | 50
Asthenia Any Severe¶ | 53 18 | 57 39 | 54 23
Stomatitis Any Grade 3/4 | 26 2 | 6 0 | 8 1
Pulmonary Any Grade 3/4 | 41 21 | 49 29 | 45 19
Nail Disorder Any Severe¶ | 11 1 | 0 0 | 2 0
Myalgia Any Severe¶ | 6 0 | 0 0 | 3 0
Arthralgia Any Severe¶ | 3 0 | 2 0 | 2 1
Taste Perversion Any Severe¶ | 6 1 | 0 0 | 0 0
* Normal Baseline LFTs: Transaminases ≤1.5 times ULN or alkaline phosphatase ≤2.5 times ULN or isolated elevations of transaminases or alkaline phosphatase up to 5 times ULN
† Febrile Neutropenia: ANC grade 4 with fever >38°C with intravenous antibiotics and/or hospitalization
¶ COSTART term and grading system‡ Not Applicable
§ Not Done

Combination therapy with DOCIVYX in chemotherapy-naïve advanced unresectable or metastatic NSCLC

Table 8 presents safety data from two arms of an open label, randomized controlled trial (TAX326) that enrolled patients with unresectable stage IIIB or IV non-small cell lung cancer and no history of prior chemotherapy. Adverse reactions were described using the NCI Common Toxicity Criteria except where otherwise noted.

Table 8: Adverse Reactions Regardless of Relationship to Treatment in Chemotherapy-Naive Advanced Non-small Cell Lung Cancer Patients Receiving DOCIVYX in Combination with Cisplatin
Adverse Reaction | DOCIVYX 75 mg/m 2 + Cisplatin 75 mg/m 2 n=406 % | Vinorelbine 25 mg/m 2 + Cisplatin 100 mg/m 2 n=396 %
Neutropenia Any Grade 3/4 | 91 74 | 90 78
Febrile Neutropenia | 5 | 5
Thrombocytopenia Any Grade 3/4 | 15 3 | 15 4
Anemia
Any | 89 | 94
Grade 3/4 | 7 | 25
Infection
Any | 35 | 37
Grade 3/4 | 8 | 8
Fever in absence of
infection
Any | 33 | 29
Grade 3/4 | <1 | 1
Hypersensitivity Reaction *
Any | 12 | 4
Grade 3/4 | 3 | <1
Fluid Retention † Any | 54 | 42
All severe or life- | 2 23 2 34 <1 15 <1 | 2 22 2 18 <1 9 <1
threatening events | 2 23 2 34 <1 15 <1 | 2 22 2 18 <1 9 <1
Pleural effusion | 2 23 2 34 <1 15 <1 | 2 22 2 18 <1 9 <1
Any | 2 23 2 34 <1 15 <1 | 2 22 2 18 <1 9 <1
All severe or life- | 2 23 2 34 <1 15 <1 | 2 22 2 18 <1 9 <1
threatening events | 2 23 2 34 <1 15 <1 | 2 22 2 18 <1 9 <1
Peripheral edema | 2 23 2 34 <1 15 <1 | 2 22 2 18 <1 9 <1
Any | 2 23 2 34 <1 15 <1 | 2 22 2 18 <1 9 <1
All severe or life- | 2 23 2 34 <1 15 <1 | 2 22 2 18 <1 9 <1
threatening events | 2 23 2 34 <1 15 <1 | 2 22 2 18 <1 9 <1
Weight gain | 2 23 2 34 <1 15 <1 | 2 22 2 18 <1 9 <1
Any | 2 23 2 34 <1 15 <1 | 2 22 2 18 <1 9 <1
All severe or life- | 2 23 2 34 <1 15 <1 | 2 22 2 18 <1 9 <1
threatening events | 2 23 2 34 <1 15 <1 | 2 22 2 18 <1 9 <1
Neurosensory
Any | 47 | 42
Grade 3/4 | 4 | 4
Neuromotor
Any | 19 | 17
Grade 3/4 | 3 | 6
Skin
Any | 16 | 14
Grade 3/4 | <1 | 1
Nausea
Any | 72 | 76
Grade 3/4 | 10 | 17
Vomiting
Any | 55 | 61
Grade 3/4 | 8 | 16
Diarrhea
Any | 47 | 25
Grade 3/4 | 7 | 3
Anorexia †
Any | 42 | 40
All severe or life- threatening events | 5 | 5
Stomatitis
Any | 24 | 21
Grade 3/4 | 2 | 1
Alopecia
Any | 75 | 42
Grade 3 | <1 | 0
Asthenia †
Any | 74 | 75
All severe or life- threatening events | 12 | 14
Nail Disorder † Any | 14 | <1
All severe events | <1 | 0
Myalgia †
Any | 18 | 12
All severe events | <1 | <1
* Replaces NCI term "Allergy"
† COSTART term and grading system

Deaths within 30 days of last study treatment occurred in 31 patients (7.6%) in the docetaxel+cisplatin arm and 37 patients (9.3%) in the vinorelbine+cisplatin arm. Deaths within 30 days of last study treatment attributed to study drug occurred in 9 patients (2.2%) in the docetaxel+cisplatin arm and 8 patients (2.0%) in the vinorelbine+cisplatin arm.

The second comparison in the study, vinorelbine+cisplatin versus DOCIVYX+carboplatin (which did not demonstrate a superior survival associated with DOCIVYX [see Clinical Studies (14.3)]) demonstrated a higher incidence of thrombocytopenia, diarrhea, fluid retention, hypersensitivity reactions, skin toxicity, alopecia and nail changes on the DOCIVYX+carboplatin arm, while a higher incidence of anemia, neurosensory toxicity, nausea, vomiting, anorexia and asthenia was observed on the vinorelbine+cisplatin arm.

Prostate Cancer

Combination therapy with DOCIVYX in patients with CRPC

The following data are based on the experience of 332 patients, who were treated with DOCIVYX 75 mg/m^2 every 3 weeks in combination with prednisone 5 mg orally twice daily (see Table 9).

Table 9: Clinically Important Treatment-Emergent Adverse Reactions (Regardless of Relationship) in Patients with Prostate Cancer Who Received DOCIVYX in Combination with Prednisone (TAX327)
 | DOCIVYX 75 mg/m^2 every 3 weeks + prednisone 5 mg twice daily n=332 % |  | Mitoxantrone 12 mg/m^2 every 3 weeks + prednisone 5 mg twice daily n=335 %
Adverse Reaction | Any | Grade 3/4 | Any | Grade 3/4
Anemia | 67 | 5 | 58 | 2
Neutropenia | 41 | 32 | 48 | 22
Thrombocytopenia | 3 | 1 | 8 | 1
Febrile neutropenia | 3 | N/A | 2 | N/A
Infection | 32 | 6 | 20 | 4
Epistaxis | 6 | 0 | 2 | 0
Allergic Reactions | 8 | 1 | 1 | 0
Fluid Retention * Weight Gain* Peripheral Edema * | 24 8 18 | 1 0 0 | 5 3 2 | 0 0 0
Neuropathy Sensory | 30 | 2 | 7 | 0
Neuropathy Motor | 7 | 2 | 3 | 1
Rash/Desquamation | 6 | 0 | 3 | 1
Alopecia | 65 | N/A | 13 | N/A
Nail Changes | 30 | 0 | 8 | 0
Nausea | 41 | 3 | 36 | 2
Diarrhea | 32 | 2 | 10 | 1
Stomatitis/Pharyngitis | 20 | 1 | 8 | 0
Taste Disturbance | 18 | 0 | 7 | 0
Vomiting | 17 | 2 | 14 | 2
Anorexia | 17 | 1 | 14 | 0
Cough | 12 | 0 | 8 | 0
Dyspnea | 15 | 3 | 9 | 1
Cardiac left ventricular function | 10 | 0 | 22 | 1
Fatigue | 53 | 5 | 35 | 5
Myalgia | 15 | 0 | 13 | 1
Tearing | 10 | 1 | 2 | 0
Arthralgia | 8 | 1 | 5 | 1
* Related to treatment

Gastric Cancer

Combination therapy with DOCIVYX in gastric adenocarcinoma

Data in the following table are based on the experience of 221 patients with advanced gastric adenocarcinoma and no history of prior chemotherapy for advanced disease who were treated with DOCIVYX 75 mg/m^2 in combination with cisplatin and fluorouracil (see Table 10).

Table 10: Clinically Important Treatment-Emergent Adverse Reactions Regardless of Relationship to Treatment in the Gastric Cancer Study
 | DOCIVYX 75 mg/m^2 + cisplatin 75 mg/m^2 + fluorouracil 750 mg/m 2 n=221 |  | Cisplatin 100 mg/m^2+ fluorouracil 1000 mg/m^2 n=224
Adverse Reaction | Any % | Grade 3/4 % | Any % | Grade 3/4 %
Anemia | 97 | 18 | 93 | 26
Neutropenia | 96 | 82 | 83 | 57
Fever in the absence of infection | 36 | 2 | 23 | 1
Thrombocytopenia | 26 | 8 | 39 | 14
Infection | 29 | 16 | 23 | 10
Febrile neutropenia | 16 | N/A | 5 | N/A
Neutropenic infection | 16 | N/A | 10 | N/A
Allergic reactions | 10 | 2 | 6 | 0
Fluid retention * | 15 | 0 | 4 | 0
Edema * | 13 | 0 | 3 | 0
Lethargy | 63 | 21 | 58 | 18
Neurosensory | 38 | 8 | 25 | 3
Neuromotor | 9 | 3 | 8 | 3
Dizziness | 16 | 5 | 8 | 2
Alopecia | 67 | 5 | 41 | 1
Rash/itch | 12 | 1 | 9 | 0
Nail changes | 8 | 0 | 0 | 0
Skin desquamation | 2 | 0 | 0 | 0
Nausea | 73 | 16 | 76 | 19
Vomiting | 67 | 15 | 73 | 19
Anorexia | 51 | 13 | 54 | 12
Stomatitis | 59 | 21 | 61 | 27
Diarrhea | 78 | 20 | 50 | 8
Constipation | 25 | 2 | 34 | 3
Esophagitis/dysphagia/odynophagia | 16 | 2 | 14 | 5
Gastrointestinal pain/cramping | 11 | 2 | 7 | 3
Cardiac dysrhythmias | 5 | 2 | 2 | 1
Myocardial ischemia | 1 | 0 | 3 | 2
Tearing | 8 | 0 | 2 | 0
Altered hearing | 6 | 0 | 13 | 2
Clinically important treatment-emergent adverse reactions were determined based upon frequency, severity, and clinical impact of the adverse reaction.
* Related to treatment

Head and Neck Cancer

Combination therapy with DOCIVYX in head and neck cancer

Table 11 summarizes the safety data obtained from patients that received induction chemotherapy with DOCIVYX 75 mg/m^2 in combination with cisplatin and fluorouracil followed by radiotherapy (TAX323; 174 patients) or chemoradiotherapy (TAX324; 251 patients). The treatment regimens are described in Section 14.6.

Table 11: Clinically Important Treatment-Emergent Adverse Reactions (Regardless of Relationship) in Patients with SCCHN Receiving Induction Chemotherapy with DOCIVYX in Combination with Cisplatin and Fluorouracil Followed by Radiotherapy (TAX323) or Chemoradiotherapy (TAX324)
 | TAX323 (n=355) |  |  |  | TAX324 (n=494)
 | DOCIVYX arm (n=174) |  | Comparator arm (n=181) |  | DOCIVYX arm (n=251) |  | Comparator arm (n=243)
Adverse Reaction (by Body System) | Any % | Grade 3/4 % | Any % | Grade 3/4 % | Any % | Grade 3/4 % | Any % | Grade 3/4 %
Neutropenia | 93 | 76 | 87 | 53 | 95 | 84 | 84 | 56
Anemia | 89 | 9 | 88 | 14 | 90 | 12 | 86 | 10
Thrombocytopenia | 24 | 5 | 47 | 18 | 28 | 4 | 31 | 11
Infection | 27 | 9 | 26 | 8 | 23 | 6 | 28 | 5
Febrile neutropenia* | 5 | N/A | 2 | N/A | 12 | N/A | 7 | N/A
Neutropenic infection | 14 | N/A | 8 | N/A | 12 | N/A | 8 | N/A
Cancer pain | 21 | 5 | 16 | 3 | 17 | 9 | 20 | 11
Lethargy | 41 | 3 | 38 | 3 | 61 | 5 | 56 | 10
Fever in the absence of infection | 32 | 1 | 37 | 0 | 30 | 4 | 28 | 3
Myalgia | 10 | 1 | 7 | 0 | 7 | 0 | 7 | 2
Weight loss | 21 | 1 | 27 | 1 | 14 | 2 | 14 | 2
Allergy | 6 | 0 | 3 | 0 | 2 | 0 | 0 | 0
Fluid retention† Edema only Weight gain only | 20 13 6 | 0 0 0 | 14 7 6 | 1 0 0 | 13 12 0 | 1 1 0 | 7 6 1 | 2 1 0
Dizziness | 2 | 0 | 5 | 1 | 16 | 4 | 15 | 2
Neurosensory | 18 | 1 | 11 | 1 | 14 | 1 | 14 | 0
Altered hearing | 6 | 0 | 10 | 3 | 13 | 1 | 19 | 3
Neuromotor | 2 | 1 | 4 | 1 | 9 | 0 | 10 | 2
Alopecia | 81 | 11 | 43 | 0 | 68 | 4 | 44 | 1
Rash/itch | 12 | 0 | 6 | 0 | 20 | 0 | 16 | 1
Dry skin | 6 | 0 | 2 | 0 | 5 | 0 | 3 | 0
Desquamation | 4 | 1 | 6 | 0 | 2 | 0 | 5 | 0
Nausea | 47 | 1 | 51 | 7 | 77 | 14 | 80 | 14
Stomatitis | 43 | 4 | 47 | 11 | 66 | 21 | 68 | 27
Vomiting | 26 | 1 | 39 | 5 | 56 | 8 | 63 | 10
Diarrhea | 33 | 3 | 24 | 4 | 48 | 7 | 40 | 3
Constipation | 17 | 1 | 16 | 1 | 27 | 1 | 38 | 1
Anorexia | 16 | 1 | 25 | 3 | 40 | 12 | 34 | 12
Esophagitis/dysphagia/Odynophagia | 13 | 1 | 18 | 3 | 25 | 13 | 26 | 10
Taste, sense of smell altered | 10 | 0 | 5 | 0 | 20 | 0 | 17 | 1
Gastrointestinal pain/cramping | 8 | 1 | 9 | 1 | 15 | 5 | 10 | 2
Heartburn | 6 | 0 | 6 | 0 | 13 | 2 | 13 | 1
Gastrointestinal bleeding | 4 | 2 | 0 | 0 | 5 | 1 | 2 | 1
Cardiac dysrhythmia | 2 | 2 | 2 | 1 | 6 | 3 | 5 | 3
Venous‡ | 3 | 2 | 6 | 2 | 4 | 2 | 5 | 4
Ischemia myocardial | 2 | 2 | 1 | 0 | 2 | 1 | 1 | 1
Tearing | 2 | 0 | 1 | 0 | 2 | 0 | 2 | 0
Conjunctivitis | 1 | 0 | 1 | 0 | 1 | 0 | 0.4 | 0
Clinically important treatment-emergent adverse reactions based upon frequency, severity, and clinical impact.
* Febrile neutropenia: grade ≥2 fever concomitant with grade 4 neutropenia requiring intravenous antibiotics and/or hospitalization.
† Related to treatment.
‡ Includes superficial and deep vein thrombosis and pulmonary embolism

6.2 Postmarketing Experience

The following adverse reactions have been identified from clinical trials and/or postmarketing surveillance. Because these reactions are reported from a population of uncertain size, it is not always possible to reliably estimate their frequency or establish a causal relationship to drug exposure.

Body as a whole: diffuse pain, chest pain, radiation recall phenomenon, injection site recall reaction (recurrence of skin reaction at a site of previous extravasation following administration of docetaxel at a different site) at the site of previous extravasation.

Cardiovascular: atrial fibrillation, deep vein thrombosis, ECG abnormalities, thrombophlebitis, pulmonary embolism, syncope, tachycardia, myocardial infarction. Ventricular arrhythmia, including ventricular tachycardia, in patients treated with docetaxel in combination regimens including doxorubicin, 5-fluorouracil and/or cyclophosphamide may be associated with fatal outcome.

Cutaneous: cutaneous lupus erythematosus, bullous eruptions such as erythema multiforme and severe cutaneous adverse reactions (SCARs) such as Stevens-Johnson syndrome, toxic epidermal necrolysis and acute generalized exanthematous pustulosis, scleroderma-like changes (usually preceded by peripheral lymphedema), severe palmar-plantar erythrodysesthesia, and permanent alopecia.

Gastrointestinal: enterocolitis, including colitis, ischemic colitis, and neutropenic enterocolitis, which may be fatal. Abdominal pain, anorexia, constipation, duodenal ulcer, esophagitis, gastrointestinal hemorrhage, gastrointestinal perforation, intestinal obstruction, ileus, and dehydration as a consequence of gastrointestinal events.

Hearing: ototoxicity, hearing disorders and/or hearing loss, including during use with other ototoxic drugs.

Hematologic: bleeding episodes, disseminated intravascular coagulation (DIC), often in association with sepsis or multiorgan failure.

Hepatic: hepatitis, sometimes fatal, primarily in patients with pre-existing liver disorders.

Hypersensitivity: anaphylactic shock with fatal outcome in patients who received premedication. Severe hypersensitivity reactions with fatal outcome with docetaxel in patients who previously experienced hypersensitivity reactions to paclitaxel.

Metabolism and nutrition disorders: electrolyte imbalance, including hyponatremia, hypokalemia, hypomagnesemia, and hypocalcemia. Tumor lysis syndrome, sometimes fatal.

Neurologic: confusion, seizures or transient loss of consciousness, sometimes appearing during the infusion of the drug.

Ophthalmologic: conjunctivitis, lacrimation or lacrimation with or without conjunctivitis, cystoid macular edema (CME). Excessive tearing which may be attributable to lacrimal duct obstruction. Transient visual disturbances (flashes, flashing lights, scotomata), typically occurring during drug infusion and reversible upon discontinuation of the infusion, in association with hypersensitivity reactions.

Respiratory: dyspnea, acute pulmonary edema, acute respiratory distress syndrome/pneumonitis, interstitial lung disease, interstitial pneumonia, respiratory failure, and pulmonary fibrosis, which may be fatal. Radiation pneumonitis in patients receiving concomitant radiotherapy.

Renal: renal insufficiency and renal failure, the majority of cases were associated with concomitant nephrotoxic drugs.

Second primary malignancies: second primary malignancies, including AML, MDS, NHL, and renal cancer [see Warnings and Precautions (5.7)].

Musculoskeletal disorder: myositis.

7 DRUG INTERACTIONS

Docetaxel is a CYP3A4 substrate. In vitro studies have shown that the metabolism of docetaxel may be modified by the concomitant administration of compounds that induce, inhibit, or are metabolized by cytochrome P450 3A4.

In vivo studies showed that the exposure of docetaxel increased 2.2-fold when it was coadministered with ketoconazole, a potent inhibitor of CYP3A4. Protease inhibitors, particularly ritonavir, may increase the exposure of docetaxel. Concomitant use of DOCIVYX and drugs that inhibit CYP3A4 may increase exposure to docetaxel and should be avoided. In patients receiving treatment with DOCIVYX, close monitoring for toxicity and a DOCIVYX dose reduction could be considered if systemic administration of a potent CYP3A4 inhibitor cannot be avoided [see Dosage and Administration (2.7), Clinical Pharmacology (12.3)].

8 USE IN SPECIFIC POPULATIONS

8.1 Pregnancy

Risk Summary

Based on findings in animal reproduction studies and its mechanism of action, DOCIVYX can cause fetal harm when administered to a pregnant woman [see Clinical Pharmacology (12.1)]. Available data from case reports in the literature and pharmacovigilance with docetaxel use in pregnant women are not sufficient to inform the drug-associated risk of major birth defects, miscarriage, or adverse maternal or fetal outcomes. DOCIVYX contains alcohol which can interfere with neurobehavioral development [see Clinical Considerations]. In animal reproductive studies, administration of docetaxel to pregnant rats and rabbits during the period of organogenesis caused an increased incidence of embryo-fetal toxicities, including intrauterine mortality, at doses as low as 0.02 and 0.003 times the recommended human dose based on body surface area, respectively [see Data]. Advise pregnant women and females of reproductive potential of the potential risk to a fetus.

The estimated background risk of major birth defects and miscarriage for the indicated populations is unknown. All pregnancies have a background risk of birth defect, miscarriage, or other adverse outcomes. In the U.S. general population, the estimated background risk of major birth defects and miscarriage in clinically recognized pregnancies is 2% to 4% and 15% to 20%, respectively.

Clinical Considerations

DOCIVYX contains alcohol [see Warnings and Precautions (5.13)]. Published studies have demonstrated that alcohol is associated with fetal harm including central nervous system abnormalities, behavioral disorders, and impaired intellectual development.

Data

Animal data

Intravenous administration of ≥0.3 and 0.03 mg/kg/day docetaxel to pregnant rats and rabbits, respectively, during the period of organogenesis caused an increased incidence of intrauterine mortality, resorptions, reduced fetal weights, and fetal ossification delays. Maternal toxicity was also observed at these doses, which were approximately 0.02 and 0.003 times the daily maximum recommended human dose based on body surface area, respectively.

8.2 Lactation

Risk Summary

There is no information regarding the presence of docetaxel in human milk, or on its effects on milk production or the breastfed child. No lactation studies in animals have been conducted. Because of the potential for serious adverse reactions in a breastfed child, advise women not to breastfeed during treatment with DOCIVYX and for 1 week after the last dose.

8.3 Females and Males of Reproductive Potential

Based on findings in animals, DOCIVYX can cause fetal harm when administered to a pregnant woman [see Use in Specific Populations (8.1)].

Pregnancy Testing

Verify pregnancy status in females of reproductive potential prior to initiating DOCIVYX.

Contraception

Females

Based on genetic toxicity findings, advise females of reproductive potential to use effective contraception during treatment and for 2 months after the last dose of DOCIVYX.

Males

Based on genetic toxicity findings, advise male patients with female partners of reproductive potential to use effective contraception during treatment and for 4 months after the last dose of DOCIVYX.

Infertility

Based on findings in animal studies, DOCIVYX may impair fertility in males of reproductive potential [see Nonclinical Toxicology (13.1)].

8.4 Pediatric Use

The alcohol content of DOCIVYX should be taken into account when given to pediatric patients [see Warnings and Precautions (5.13)].

The efficacy of DOCIVYX in pediatric patients as monotherapy or in combination has not been established. The overall safety profile of DOCIVYX in pediatric patients receiving monotherapy or TCF was consistent with the known safety profile in adults.

DOCIVYX has been studied in a total of 289 pediatric patients: 239 in 2 trials with monotherapy and 50 in combination treatment with cisplatin and 5-fluorouracil (TCF).

DOCIVYX Monotherapy

DOCIVYX monotherapy was evaluated in a dose-finding phase 1 trial in 61 pediatric patients (median age 12.5 years, range 1–22 years) with a variety of refractory solid tumors. The recommended dose was 125 mg/m^2 as a 1-hour intravenous infusion every 21 days. The primary dose limiting toxicity was neutropenia.

The recommended dose for DOCIVYX monotherapy was evaluated in a phase 2 single-arm trial in 178 pediatric patients (median age 12 years, range 1–26 years) with a variety of recurrent/refractory solid tumors. Efficacy was not established with tumor response rates ranging from one complete response (CR) (0.6%) in a patient with undifferentiated sarcoma to four partial responses (2.2%) seen in one patient each with Ewing Sarcoma, neuroblastoma, osteosarcoma, and squamous cell carcinoma.

DOCIVYX in Combination

DOCIVYX was studied in combination with cisplatin and 5-fluorouracil (TCF) versus cisplatin and 5- fluorouracil (CF) for the induction treatment of nasopharyngeal carcinoma (NPC) in pediatric patients prior to chemoradiation consolidation. Seventy-five patients (median age 16 years, range 9 to 21 years) were randomized (2:1) to DOCIVYX (75 mg/m^2) in combination with cisplatin (75 mg/m2) and 5- fluorouracil (750 mg/m^2) (TCF) or to cisplatin (80 mg/m^2) and 5-fluorouracil (1000 mg/m^2/day) (CF). The primary endpoint was the CR rate following induction treatment of NPC. One patient out of 50 in the TCF group (2%) had a complete response while none of the 25 patients in the CF group had a complete response.

Pharmacokinetics

Pharmacokinetic parameters for docetaxel were determined in 2 pediatric solid tumor trials. Following docetaxel administration at 55 mg/m^2 to 235 mg/m^2 in a 1-hour intravenous infusion every 3 weeks in 25 patients aged 1 to 20 years (median 11 years), docetaxel clearance was 17.3±10.9 L/h/m^2.

Docetaxel was administered in combination with cisplatin and 5-fluorouracil (TCF), at dose levels of 75 mg/m^2 in a 1-hour intravenous infusion day 1 in 28 patients aged 10 to 21 years (median 16 years, 17 patients were older than 16). Docetaxel clearance was 17.9±8.75 L/h/m^2, corresponding to an AUC of 4.20±2.57 μg·h/mL.

In summary, the body surface area adjusted clearance of docetaxel monotherapy and TCF combination in children were comparable to those in adults [see Clinical Pharmacology (12.3)].

8.5 Geriatric Use

In general, dose selection for an elderly patient should be cautious, reflecting the greater frequency of decreased hepatic, renal, or cardiac function and of concomitant disease or other drug therapy in elderly patients.

Non-small Cell Lung Cancer

In a study conducted in chemotherapy-naive patients with NSCLC (TAX326), 148 patients (36%) in the DOCIVYX+cisplatin group were 65 years of age or greater. There were 128 patients (32%) in the vinorelbine+cisplatin group 65 years of age or greater. In the DOCIVYX+cisplatin group, patients less than 65 years of age had a median survival of 10.3 months (95% CI: 9.1 months, 11.8 months) and patients 65 years or older had a median survival of 12.1 months (95% CI: 9.3 months, 14 months). In patients 65 years of age or greater treated with DOCIVYX+cisplatin, diarrhea (55%), peripheral edema (39%) and stomatitis (28%) were observed more frequently than in the vinorelbine+cisplatin group (diarrhea 24%, peripheral edema 20%, stomatitis 20%). Patients treated with DOCIVYX+cisplatin who were 65 years of age or greater were more likely to experience diarrhea (55%), infections (42%), peripheral edema (39%) and stomatitis (28%) compared to patients less than the age of 65 administered the same treatment (43%, 31%, 31% and 21%, respectively).

When DOCIVYX was combined with carboplatin for the treatment of chemotherapy-naive, advanced non-small cell lung carcinoma, patients 65 years of age or greater (28%) experienced higher frequency of infection compared to similar patients treated with DOCIVYX+cisplatin, and a higher frequency of diarrhea, infection and peripheral edema than elderly patients treated with vinorelbine+cisplatin.

Prostate Cancer

Of the 333 patients treated with DOCIVYX every three weeks plus prednisone in the CRPC study (TAX327), 209 patients were 65 years of age or greater and 68 patients were older than 75 years. In patients treated with DOCIVYX every three weeks, the following treatment-emergent adverse reactions occurred at rates ≥10% higher in patients 65 years of age or greater compared to younger patients: anemia (71% vs 59%), infection (37% vs 24%), nail changes (34% vs 23%), anorexia (21% vs 10%), weight loss (15% vs 5%), respectively.

Breast Cancer

In the adjuvant breast cancer trial (TAX316), DOCIVYX in combination with doxorubicin and cyclophosphamide was administered to 744 patients of whom 48 (6%) were 65 years of age or greater. The number of elderly patients who received this regimen was not sufficient to determine whether there were differences in safety and efficacy between elderly and younger patients.

Gastric Cancer

Among the 221 patients treated with DOCIVYX in combination with cisplatin and fluorouracil in the gastric cancer study, 54 were 65 years of age or older and 2 patients were older than 75 years. In this study, the number of patients who were 65 years of age or older was insufficient to determine whether they respond differently from younger patients. However, the incidence of serious adverse reactions was higher in the elderly patients compared to younger patients. The incidence of the following adverse reactions (all grades, regardless of relationship): lethargy, stomatitis, diarrhea, dizziness, edema, febrile neutropenia/neutropenic infection occurred at rates ≥10% higher in patients who were 65 years of age or older compared to younger patients. Elderly patients treated with TCF should be closely monitored.

Head and Neck Cancer

Among the 174 and 251 patients who received the induction treatment with DOCIVYX in combination with cisplatin and fluorouracil (TPF) for SCCHN in the TAX323 and TAX324 studies, 18 (10%) and 32 (13%) of the patients were 65 years of age or older, respectively.

These clinical studies of DOCIVYX in combination with cisplatin and fluorouracil in patients with SCCHN did not include sufficient numbers of patients aged 65 and over to determine whether they respond differently from younger patients. Other reported clinical experience with this treatment regimen has not identified differences in responses between elderly and younger patients.

8.6 Hepatic Impairment

Avoid DOCIVYX in patients with bilirubin >ULN and patients with AST and/or ALT >1.5 × ULN concomitant with alkaline phosphatase >2.5 × ULN [see Boxed Warning, Warnings and Precautions (5.2), Clinical Pharmacology (12.3)].

The alcohol content of DOCIVYX should be taken into account when given to patients with hepatic impairment [see Warnings and Precautions (5.13)].

10 OVERDOSAGE

There is no known antidote for DOCIVYX overdosage. In case of overdosage, the patient should be kept in a specialized unit where vital functions can be closely monitored. Anticipated complications of overdosage include: bone marrow suppression, peripheral neurotoxicity, and mucositis. Patients should receive therapeutic G-CSF as soon as possible after discovery of overdose. Other appropriate symptomatic measures should be taken, as needed.

In two reports of overdose, one patient received 150 mg/m^2 and the other received 200 mg/m^2 as 1-hour infusions. Both patients experienced severe neutropenia, mild asthenia, cutaneous reactions, and mild paresthesia, and recovered without incident.

In mice, lethality was observed following single intravenous doses that were ≥154 mg/kg (about 4.5 times the human dose of 100 mg/m^2 on a mg/m^2 basis); neurotoxicity associated with paralysis, non- extension of hind limbs, and myelin degeneration was observed in mice at 48 mg/kg (about 1.5 times the human dose of 100 mg/m^2 basis). In male and female rats, lethality was observed at a dose of 20 mg/kg (comparable to the human dose of 100 mg/m^2 on a mg/m^2 basis) and was associated with abnormal mitosis and necrosis of multiple organs.

11 DESCRIPTION

Docetaxel is an antineoplastic agent belonging to the taxoid family. It is prepared by semisynthesis beginning with a precursor extracted from the renewable needle biomass of yew plants. The chemical name for docetaxel is (2R,3S)-N-carboxy-3-phenylisoserine, N-tert-butyl ester, 13-ester with 5β-20- epoxy-1,2α,4,7β,10β,13α-hexahydroxytax-11-en-9-one 4-acetate 2-benzoate, trihydrate. Docetaxel has the following structural formula:

Docetaxel is a white to almost-white powder with an empirical formula of C43H53NO14·3H2O, and a molecular weight of 861.9. It is highly lipophilic and practically insoluble in water.

DOCIVYX (docetaxel) Injection is a sterile, non-pyrogenic, pale-yellow to brownish-yellow solution at 10 mg/mL concentration.

Each mL contains 10 mg docetaxel (anhydrous), 0.38 grams of sulfoxybutyl ether cyclodextrin (SBECD), 0.16 grams of polyethylene glycol 300, 40 mg of polyvinylpyrrolidone k12, and 0.22 grams of dehydrated alcohol in water for injection, with citric acid for pH adjustment.

DOCIVYX is available in single-dose vials containing 20 mg (2 mL), 80 mg (8 mL) or 160 mg (16 mL) docetaxel (anhydrous).

DOCIVYX requires NO prior dilution with a diluent and is ready to add to the infusion solution.

12 CLINICAL PHARMACOLOGY

12.1 Mechanism of Action

Docetaxel is an antineoplastic agent that acts by disrupting the microtubular network in cells that is essential for mitotic and interphase cellular functions. Docetaxel binds to free tubulin and promotes the assembly of tubulin into stable microtubules while simultaneously inhibiting their disassembly. This leads to the production of microtubule bundles without normal function and to the stabilization of microtubules, which results in the inhibition of mitosis in cells. Docetaxel's binding to microtubules does not alter the number of protofilaments in the bound microtubules, a feature which differs from most spindle poisons currently in clinical use.

12.3 Pharmacokinetics

Absorption

The pharmacokinetics of docetaxel has been evaluated in cancer patients after administration of 20 mg/m^2 to 115 mg/m^2 in phase 1 studies. The area under the curve (AUC) was dose proportional following doses of 70 mg/m^2 to 115 mg/m^2 with infusion times of 1 to 2 hours. Docetaxel's pharmacokinetic profile is consistent with a three-compartment pharmacokinetic model, with initial rapid distribution phase and the late (terminal) phase.

Distribution

Mean steady state volume of distribution was 113 L. Docetaxel is approximately 94% protein bound in vitro, mainly to α1-acid glycoprotein, albumin, and lipoproteins. In three cancer patients, the in vitro binding to plasma proteins was approximately 97%. Dexamethasone does not affect the protein binding of docetaxel.

Elimination

With extended plasma sampling up to 8 to 22 days post infusion, the estimated mean total body clearance was 18 L/h/m^2(range of means: 14 to 23) and mean terminal elimination half-life was 116 hours (range of means: 92 to 135).

Metabolism

Docetaxel is metabolized by the CYP3A4 isoenzyme in vitro [see Drug Interactions (7)].

Excretion

In three cancer patients, urinary and fecal excretion accounted for approximately 6% and 75% of the administered radioactivity, respectively, within 7 days. About 80% of the radioactivity recovered in feces was excreted during the first 48 hours as 1 major and 3 minor metabolites with less than 8% as unchanged drug.

Specific Populations

Effect of Age: A population pharmacokinetic analysis was carried out after DOCIVYX treatment of 535 patients dosed at 100 mg/m^2. Pharmacokinetic parameters estimated by this analysis were very close to those estimated from phase 1 studies. The pharmacokinetics of docetaxel was not influenced by age.

Effect of Gender: The population pharmacokinetics analysis described above also indicated that gender did not influence the pharmacokinetics of docetaxel.

Hepatic Impairment: The population pharmacokinetic analysis described above indicated that in patients with clinical chemistry data suggestive of mild to moderate liver impairment (AST and/or ALT >1.5 times ULN concomitant with alkaline phosphatase >2.5 times ULN), total body clearance was lowered by an average of 27%, resulting in a 38% increase in systemic exposure (AUC). This average, however, includes a substantial range and there is, at present, no measurement that would allow recommendation for dose adjustment in such patients. Patients with combined abnormalities of transaminase and alkaline phosphatase should not be treated with DOCIVYX. Patients with severe hepatic impairment have not been studied [see Warnings and Precautions (5.2), Use in Specific Populations (8.6)].

Effect of Race: Mean total body clearance for Japanese patients dosed at the range of 10 mg/m^2 to 90 mg/m^2 was similar to that of European/American populations dosed at 100 mg/m^2, suggesting no significant difference in the elimination of docetaxel in the two populations.

Drug Interaction Studies

Effect of Ketoconazole: The effect of ketoconazole (a strong CYP3A4 inhibitor) on the pharmacokinetics of docetaxel was investigated in 7 cancer patients. Patients were randomized to receive either docetaxel (100 mg/m2 intravenous) alone or docetaxel (10 mg/m2 intravenous) in combination with ketoconazole (200 mg orally once daily for 3 days) in a crossover design with a 3- week washout period. The results of this study indicated that the mean dose-normalized AUC of docetaxel was increased 2.2-fold and its clearance was reduced by 49% when docetaxel was coadministered with ketoconazole [see Dosage and Administration (2.7), Drug Interactions (7)].

Effect of combination therapies

- Dexamethasone: Docetaxel total body clearance was not modified by pretreatment with dexamethasone.
- Cisplatin: Clearance of docetaxel in combination therapy with cisplatin was similar to that previously observed following monotherapy with docetaxel. The pharmacokinetic profile of cisplatin in combination therapy with docetaxel was similar to that observed with cisplatin alone.
- Cisplatin and Fluorouracil: The combined administration of docetaxel, cisplatin and fluorouracil in 12 patients with solid tumors had no influence on the pharmacokinetics of each individual drug.
- Prednisone: A population pharmacokinetic analysis of plasma data from 40 patients with metastatic CRPC indicated that docetaxel systemic clearance in combination with prednisone is similar to that observed following administration of docetaxel alone.
- Cyclophosphamide and Doxorubicin: A study was conducted in 30 patients with advanced breast cancer to determine the potential for drug-drug interactions between docetaxel (75 mg/m^2), doxorubicin (50 mg/m^2), and cyclophosphamide (500 mg/m^2) when administered in combination. The coadministration of docetaxel had no effect on the pharmacokinetics of doxorubicin and cyclophosphamide when the three drugs were given in combination compared to coadministration of doxorubicin and cyclophosphamide only. In addition, doxorubicin and cyclophosphamide had no effect on docetaxel plasma clearance when the three drugs were given in combination compared to historical data for docetaxel monotherapy.

13 NONCLINICAL TOXICOLOGY

13.1 Carcinogenesis, Mutagenesis, Impairment of Fertility

Carcinogenicity studies with docetaxel have not been performed.

Docetaxel was genotoxic by an aneugenic mechanism in the in vitro chromosome aberration test in CHO-K1 cells and in the in vivo micronucleus test in mice administered doses of 0.39 to 1.56 mg/kg (about 1/60th to 1/15th the recommended human dose on a mg/m^2 basis). Docetaxel was not mutagenic in the Ames test or the CHO/HGPRT gene mutation assays.

Docetaxel did not reduce fertility in rats when administered in multiple intravenous doses of up to 0.3 mg/kg (about 1/50th the recommended human dose on a mg/m^2 basis), but decreased testicular weights were reported. This correlates with findings of a 10-cycle toxicity study (dosing once every 21 days for 6 months) in rats and dogs in which testicular atrophy or degeneration was observed at intravenous doses of 5 mg/kg in rats and 0.375 mg/kg in dogs (about 1/3rd and 1/15th the recommended human dose on a mg/m^2 basis, respectively). An increased frequency of dosing in rats produced similar effects at lower dose levels.

14 CLINICAL STUDIES

14.1 Locally Advanced or Metastatic Breast Cancer

The efficacy and safety of DOCIVYX have been evaluated in locally advanced or metastatic breast cancer after failure of previous chemotherapy (alkylating agent–containing regimens or anthracycline- containing regimens).

Randomized Trials

In one randomized trial, patients with a history of prior treatment with an anthracycline-containing regimen were assigned to treatment with DOCIVYX (100 mg/m^2 every 3 weeks) or the combination of mitomycin (12 mg/m^2 every 6 weeks) and vinblastine (6 mg/m2 every 3 weeks). Two hundred three patients were randomized to DOCIVYX and 189 to the comparator arm. Most patients had received prior chemotherapy for metastatic disease; only 27 patients on the DOCIVYX arm and 33 patients on the comparator arm entered the study following relapse after adjuvant therapy. Three-quarters of patients had measurable, visceral metastases. The primary endpoint was time to progression. The following table summarizes the study results. (See Table 12.)

Table 12: Efficacy of DOCIVYX in the Treatment of Breast Cancer Patients Previously Treated with an Anthracycline-Containing Regimen (Intent-to-Treat Analysis)
Efficacy Parameter | Docetaxel (n=203) | Mitomycin/Vinblastine (n=189) | p-value
Median Survival | 11.4 months | 8.7 months | p=0.01 Log Rank
Risk Ratio*, Mortality (Docetaxel: Control) 95% CI (Risk Ratio) | 0.73 0.58–0.93 |  | p=0.01 Log Rank
Median Time to Progression | 4.3 months | 2.5 months | p=0.01 Log Rank
Risk Ratio*, Progression (Docetaxel: Control) 95% CI (Risk Ratio) | 0.75 0.61–0.94 |  | p=0.01 Log Rank
Overall Response Rate Complete Response Rate | 28.1% 3.4% | 9.5% 1.6% | p<0.0001 Chi Square
* For the risk ratio, a value less than 1.00 favors docetaxel.

In a second randomized trial, patients previously treated with an alkylating-containing regimen were assigned to treatment with DOCIVYX (100 mg/m^2) or doxorubicin (75 mg/m^2) every 3 weeks. One hundred sixty-one patients were randomized to DOCIVYX and 165 patients to doxorubicin.

Approximately one-half of patients had received prior chemotherapy for metastatic disease, and one- half entered the study following relapse after adjuvant therapy. Three-quarters of patients had measurable, visceral metastases. The primary endpoint was time to progression. The study results are summarized below. (See Table 13.)

Table 13: Efficacy of DOCIVYX in the Treatment of Breast Cancer Patients Previously Treated with an Alkylating-Containing Regimen (Intent-to-Treat Analysis)
Efficacy Parameter | Docetaxel (n=161) | Doxorubicin (n=165) | p-value
Median Survival | 14.7 months | 14.3 months | p=0.39 Log Rank
Risk Ratio*, Mortality (Docetaxel: Control) 95% CI (Risk Ratio) | 0.89 0.68–1.16 |  | p=0.39 Log Rank
Median Time to Progression | 6.5 months | 5.3 months | p=0.45 Log Rank
Risk Ratio*, Progression (Docetaxel: Control) 95% CI (Risk Ratio) | 0.93 0.71–1.16 |  | p=0.45 Log Rank
Overall Response Rate | 45.3% | 29.7% | p=0.004
Complete Response Rate | 6.8% | 4.2% | Chi Square
* For the risk ratio, a value less than 1.00 favors docetaxel.

In another multicenter open-label, randomized trial (TAX313), in the treatment of patients with advanced breast cancer who progressed or relapsed after one prior chemotherapy regimen, 527 patients were randomized to receive DOCIVYX monotherapy 60 mg/m^2 (n=151), 75 mg/m^2 (n=188) or 100 mg/m^2 (n=188). In this trial, 94% of patients had metastatic disease and 79% had received prior anthracycline therapy. Response rate was the primary endpoint. Response rates increased with DOCIVYX dose: 19.9% for the 60 mg/m^2 group compared to 22.3% for the 75 mg/m^2 and 29.8% for the 100 mg/m^2 group; pair-wise comparison between the 60 mg/m^2 and 100 mg/m^2 groups was statistically significant (p=0.037).

Single Arm Studies

DOCIVYX at a dose of 100 mg/m^2 was studied in six single arm studies involving a total of 309 patients with metastatic breast cancer in whom previous chemotherapy had failed. Among these, 190 patients had anthracycline-resistant breast cancer, defined as progression during an anthracycline- containing chemotherapy regimen for metastatic disease, or relapse during an anthracycline-containing adjuvant regimen. In anthracycline-resistant patients, the overall response rate was 37.9% (72/190; 95% CI: 31.0–44.8) and the complete response rate was 2.1%.

DOCIVYX was also studied in three single arm Japanese studies at a dose of 60 mg/m^2, in 174 patients who had received prior chemotherapy for locally advanced or metastatic breast cancer. Among 26 patients whose best response to an anthracycline had been progression, the response rate was 34.6% (95% CI: 17.2–55.7), similar to the response rate in single arm studies of 100 mg/m^2.

14.2 Adjuvant Treatment of Breast Cancer

A multicenter, open-label, randomized trial (TAX316) evaluated the efficacy and safety of DOCIVYX for the adjuvant treatment of patients with axillary-node-positive breast cancer and no evidence of distant metastatic disease. After stratification according to the number of positive lymph nodes (1–3, 4+), 1491 patients were randomized to receive either DOCIVYX 75 mg/m^2 administered 1-hour after doxorubicin 50 mg/m^2 and cyclophosphamide 500 mg/m^2 (TAC arm), or doxorubicin 50 mg/m^2 followed by fluorouracil 500 mg/m^2 and cyclophosphamide 500 mg/m^2 (FAC arm). Both regimens were administered every 3 weeks for 6 cycles. DOCIVYX was administered as a 1-hour infusion; all other drugs were given as intravenous bolus on day 1. In both arms, after the last cycle of chemotherapy, patients with positive estrogen and/or progesterone receptors received tamoxifen 20 mg daily for up to 5 years. Adjuvant radiation therapy was prescribed according to guidelines in place at participating institutions and was given to 69% of patients who received TAC and 72% of patients who received FAC.

Results from a second interim analysis (median follow-up 55 months) are as follows: In study TAX316, the docetaxel-containing combination regimen TAC showed significantly longer disease-free survival (DFS) than FAC (hazard ratio=0.74; 2-sided 95% CI=0.60, 0.92, stratified log rank p=0.0047). The primary endpoint, disease-free survival, included local and distant recurrences, contralateral breast cancer and deaths from any cause. The overall reduction in risk of relapse was 25.7% for TAC-treated patients. (See Figure 1.)

At the time of this interim analysis, based on 219 deaths, overall survival was longer for TAC than FAC (hazard ratio=0.69, 2-sided 95% CI=0.53, 0.90). (See Figure 2.) There will be further analysis at the time survival data mature.

Figure 1: TAX316 Disease-Free Survival K-M curve
Figure 2: TAX316 Overall Survival K-M Curve

The following table describes the results of subgroup analyses for DFS and OS (see Table 14).

Table 14: Subset Analyses-Adjuvant Breast Cancer Study
Patient subset | Number of patients | Disease-Free Survival |  | Overall Survival
Patient subset | Number of patients | Hazard ratio * | 95% CI | Hazard ratio * | 95% CI
No. of positive nodes Overall 1–3 4+ | 744 467 277 | 0.74 0.64 0.84 | (0.60, 0.92) (0.47, 0.87) (0.63, 1.12) | 0.69 0.45 0.93 | (0.53, 0.90) (0.29, 0.70) (0.66, 1.32)
Receptor status Positive Negative | 566 178 | 0.76 0.68 | (0.59, 0.98) (0.48, 0.97) | 0.69 0.66 | (0.48, 0.99) (0.44, 0.98)
* a hazard ratio of less than 1 indicates that TAC is associated with a longer disease-free survival or overall survival compared to FAC.

14.3 Non-small Cell Lung Cancer (NSCLC)

The efficacy and safety of DOCIVYX has been evaluated in patients with unresectable, locally advanced or metastatic non-small cell lung cancer whose disease has failed prior platinum-based chemotherapy or in patients who are chemotherapy naive.

Monotherapy with DOCIVYX for NSCLC Previously Treated with Platinum-Based Chemotherapy

Two randomized, controlled trials established that a DOCIVYX dose of 75 mg/m^2 was tolerable and yielded a favorable outcome in patients previously treated with platinum-based chemotherapy (see below). DOCIVYX at a dose of 100 mg/m^2, however, was associated with unacceptable hematologic toxicity, infections, and treatment-related mortality and this dose should not be used [see Boxed Warning, Dosage and Administration (2.7), Warnings and Precautions (5.3)].

One trial (TAX317), randomized patients with locally advanced or metastatic non-small cell lung cancer, a history of prior platinum-based chemotherapy, no history of taxane exposure, and an ECOG performance status ≤2 to DOCIVYX or best supportive care. The primary endpoint of the study was survival. Patients were initially randomized to DOCIVYX 100 mg/m^2 or best supportive care, but early toxic deaths at this dose led to a dose reduction to DOCIVYX 75 mg/m^2. A total of 104 patients were randomized in this amended study to either DOCIVYX 75 mg/m2 or best supportive care.

In a second randomized trial (TAX320), 373 patients with locally advanced or metastatic non-small cell lung cancer, a history of prior platinum-based chemotherapy, and an ECOG performance status ≤2 were randomized to DOCIVYX 75 mg/m^2, DOCIVYX 100 mg/m^2 and a treatment in which the investigator chose either vinorelbine 30 mg/m^2 days 1, 8, and 15 repeated every 3 weeks or ifosfamide 2 g/m^2 days 1–3 repeated every 3 weeks. Forty percent of the patients in this study had a history of prior paclitaxel exposure. The primary endpoint was survival in both trials. The efficacy data for the DOCIVYX 75 mg/m^2 arm and the comparator arms are summarized in Table 15 and Figures 3 and 4 showing the survival curves for the two studies.

Table 15: Efficacy of DOCIVYX in the Treatment of Non-small Cell Lung Cancer Patients Previously Treated with a Platinum-Based Chemotherapy Regimen (Intent-to-Treat Analysis)
 | TAX317 |  | TAX320
 | Docetaxel 75 mg/m^2 n=55 | Best Supportive Care n=49 | Docetaxel 75 mg/m^2 n=55 | Control (V/I*) n=123
Overall Survival Log-rank Test | p=0.01 |  | p=0.13
Risk Ratio†, Mortality (Docetaxel: Control) 95% CI (Risk Ratio) | 0.56 (0.35, 0.88) |  | 0.82 (0.63, 1.06)
Median Survival 95% CI | 7.5 months‡ (5.5, 12.8) | 4.6 months (3.7, 6.1) | 5.7 months (5.1, 7.1) | 5.6 months (4.4, 7.9)
% 1-year Survival 95% CI | 37%‡§ (24, 50) | 12% (2, 23) | 30%‡§ (22, 39) | 20% (13, 27)
Time to Progression 95% CI | 12.3 weeks‡ (9.0, 18.3) | 7.0 weeks (6.0, 9.3) | 8.3 weeks (7.0, 11.7) | 7.6 weeks (6.7, 10.1)
Response Rate 95% CI | 5.5% (1.1, 15.1) | Not Applicable | 5.7% (2.3, 11.3) | 0.8% (0.0, 4.5)
*Vinorelbine/Ifosfamide
‡ p≤0.05
§ uncorrected for multiple comparisons
† a value less than 1.00 favors docetaxel

Only one of the two trials (TAX317) showed a clear effect on survival, the primary endpoint; that trial also showed an increased rate of survival to one year. In the second study (TAX320) the rate of survival at one year favored DOCIVYX 75 mg/m^2.

Figure 3: TAX317 Survival K-M Curves - DOCIVYX 75 mg/m2 Versus Best Supportive Care
Figure 4: TAX320 Survival K-M Curves - DOCIVYX 75 mg/m2 Versus Vinorelbine or Ifosfamide Control

Patients treated with DOCIVYX at a dose of 75 mg/m^2 experienced no deterioration in performance status and body weight relative to the comparator arms used in these trials.

Combination Therapy with DOCIVYX for Chemotherapy-Naive NSCLC

In a randomized controlled trial (TAX326), 1218 patients with unresectable stage IIIB or IV NSCLC and no prior chemotherapy were randomized to receive one of three treatments: DOCIVYX 75 mg/m^2 as a 1-hour infusion immediately followed by cisplatin 75 mg/m^2 over 30 to 60 minutes every 3 weeks; vinorelbine 25 mg/m^2 administered over 6–10 minutes on days 1, 8, 15, 22 followed by cisplatin 100 mg/m^2 administered on day 1 of cycles repeated every 4 weeks; or a combination of DOCIVYX and carboplatin.

The primary efficacy endpoint was overall survival. Treatment with DOCIVYX+cisplatin did not result in a statistically significantly superior survival compared to vinorelbine+cisplatin (see table below). The 95% confidence interval of the hazard ratio (adjusted for interim analysis and multiple comparisons) shows that the addition of DOCIVYX to cisplatin results in an outcome ranging from a 6% inferior to a 26% superior survival compared to the addition of vinorelbine to cisplatin. The results of a further statistical analysis showed that at least (the lower bound of the 95% confidence interval) 62% of the known survival effect of vinorelbine when added to cisplatin (about a 2-month increase in median survival; Wozniak et al. JCO, 1998) was maintained. The efficacy data for the DOCIVYX+cisplatin arm and the comparator arm are summarized in Table 16.

Table 16: Survival Analysis of DOCIVYX in Combination Therapy for Chemotherapy-Naive NSCLC
Comparison | DOCIVYX + Cisplatin n=408 | Vinorelbine + Cisplatin n=405
Kaplan-Meier Estimate of Median Survival | 10.9 months | 10.0 months
p-value* | 0.122
Estimated Hazard Ratio† | 0.88
Adjusted 95% CI‡ | (0.74, 1.06)
* From the superiority test (stratified log rank) comparing DOCIVYX+cisplatin to vinorelbine+cisplatin
† Hazard ratio of DOCIVYX+cisplatin versus vinorelbine+cisplatin. A hazard ratio of less than 1 indicates that DOCIVYX+cisplatin is associated with a longer survival.
‡ Adjusted for interim analysis and multiple comparisons.

The second comparison in the same three-arm study, vinorelbine+cisplatin versus DOCIVYX+carboplatin, did not demonstrate superior survival associated with the DOCIVYX arm (Kaplan-Meier estimate of median survival was 9.1 months for DOCIVYX+carboplatin compared to 10.0 months on the vinorelbine+cisplatin arm) and the DOCIVYX+carboplatin arm did not demonstrate preservation of at least 50% of the survival effect of vinorelbine added to cisplatin. Secondary endpoints evaluated in the trial included objective response and time to progression. There was no statistically significant difference between DOCIVYX+cisplatin and vinorelbine+cisplatin with respect to objective response and time to progression (see Table 17).

Table 17: Response and TTP Analysis of DOCIVYX in Combination Therapy for Chemotherapy-Naive NSCLC
Endpoint | DOCIVYX + Cisplatin | Vinorelbine + Cisplatin | p-value
Objective Response Rate (95% CI)* | 31.6% (26.5%, 36.8%) | 24.4% (19.8%, 29.2%) | Not Significant
Median Time to Progression† (95% CI)* | 21.4 weeks (19.3, 24.6) | 22.1 weeks (18.1, 25.6) | Not Significant
*Adjusted for multiple comparisons.
† Kaplan- Meier estimates.

14.4 Castration-Resistant Prostate Cancer (CRPC)

The safety and efficacy of DOCIVYX in combination with prednisone in patients with metastatic CRPC were evaluated in a randomized multicenter active control trial. A total of 1006 patients with Karnofsky Performance Status (KPS) ≥60 were randomized to the following treatment groups:

- DOCIVYX 75 mg/m^2every 3 weeks for 10 cycles.
- DOCIVYX 30 mg/m^2administered weekly for the first 5 weeks in a 6-week cycle for 5 cycles.
- Mitoxantrone 12 mg/m^2every 3 weeks for 10 cycles.

All 3 regimens were administered in combination with prednisone 5 mg twice daily, continuously.

In the DOCIVYX every three week arm, a statistically significant overall survival advantage was demonstrated compared to mitoxantrone. In the DOCIVYX weekly arm, no overall survival advantage was demonstrated compared to the mitoxantrone control arm. Efficacy results for the DOCIVYX every 3 week arm versus the control arm are summarized in Table 18 and Figure 5.

Table 18: Efficacy of DOCIVYX in the Treatment of Patients with Metastatic Castration-Resistant Prostate Cancer (Intent-to-Treat Analysis)
 | DOCIVYX + Prednisone every 3 weeks | Mitoxantrone + Prednisone every 3 weeks
Number of patients | 335 | 337
Median survival (months) | 18.9 | 16.5
95% CI | (17.0–21.2) | (14.4–18.6)
Hazard ratio | 0.761 | --
95% CI | (0.619–0.936) | --
p-value* | 0.0094 | --
* Stratified log- rank test. Threshold for statistical significance = 0.0175 because of 3 arms.

Figure 5: TAX327 Survival K-M Curves

14.5 Gastric Adenocarcinoma

A multicenter, open-label, randomized trial was conducted to evaluate the safety and efficacy of DOCIVYX for the treatment of patients with advanced gastric adenocarcinoma, including adenocarcinoma of the gastroesophageal junction, who had not received prior chemotherapy for advanced disease. A total of 445 patients with KPS >70 were treated with either DOCIVYX (T) (75 mg/m^2 on day 1) in combination with cisplatin (C) (75 mg/m^2 on day 1) and fluorouracil (F) (750 mg/m^2 per day for 5 days) or cisplatin (100 mg/m^2 on day 1) and fluorouracil (1000 mg/m^2 per day for 5 days). The length of a treatment cycle was 3 weeks for the TCF arm and 4 weeks for the CF arm. The demographic characteristics were balanced between the two treatment arms. The median age was 55 years, 71% were male, 71% were Caucasian, 24% were 65 years of age or older, 19% had a prior curative surgery and 12% had palliative surgery. The median number of cycles administered per patient was 6 (with a range of 1–16) for the TCF arm compared to 4 (with a range of 1–12) for the CF arm.

Time to progression (TTP) was the primary endpoint and was defined as time from randomization to disease progression or death from any cause within 12 weeks of the last evaluable tumor assessment or within 12 weeks of the first infusion of study drugs for patients with no evaluable tumor assessment after randomization. The hazard ratio (HR) for TTP was 1.47 (CF/TCF, 95% CI: 1.19–1.83) with a significantly longer TTP (p=0.0004) in the TCF arm. Approximately 75% of patients had died at the time of this analysis. Overall survival was significantly longer (p=0.0201) in the TCF arm with a HR of 1.29 (95% CI: 1.04–1.61). Efficacy results are summarized in Table 19 and Figures 6 and 7.

Table 19: Efficacy of DOCIVYX in the Treatment of Patients with Gastric Adenocarcinoma
Endpoint | TCF n=221 | CF n=224
Median TTP (months) (95% CI) Hazard ratio* (95% CI) †p-value | 5.6 (4.86–5.91) | 3.7 (3.45–4.47)
Median TTP (months) (95% CI) Hazard ratio* (95% CI) †p-value | 0.68 (0.55–0.84) 0.0004
Median survival (months) (95% CI) Hazard ratio* (95% CI) †p-value | 9.2 (8.38–10.58) | 8.6 (7.16–9.46)
Median survival (months) (95% CI) Hazard ratio* (95% CI) †p-value | 0.77 (0.62–0.96) 0.0201
Overall Response Rate (CR+PR) (%) p-value | 36.7 | 25.4
Overall Response Rate (CR+PR) (%) p-value | 0.0106
† Unstratified log- rank test
* For the hazard ratio (TCF/CF), values less than 1.00 favor the DOCIVYX arm.

Subgroup analyses were consistent with the overall results across age, gender and race.

Figure 6: Gastric Cancer Study (TAX325) Time to Progression K-M Curve
Figure 7: Gastric Cancer Study (TAX325) Survival K-M Curve

14.6 Head and Neck Cancer

Induction Chemotherapy Followed by Radiotherapy (TAX323)

The safety and efficacy of DOCIVYX in the induction treatment of patients with squamous cell carcinoma of the head and neck (SCCHN) was evaluated in a multicenter, open-label, randomized trial (TAX323). In this study, 358 patients with inoperable locally advanced SCCHN, and WHO performance status 0 or 1, were randomized to one of two treatment arms. Patients on the DOCIVYX arm received DOCIVYX (T) 75 mg/m^2 followed by cisplatin (P) 75 mg/m^2 on Day 1, followed by fluorouracil (F) 750 mg/m^2 per day as a continuous infusion on Days 1–5. The cycles were repeated every three weeks for 4 cycles. Patients whose disease did not progress received radiotherapy (RT) according to institutional guidelines (TPF/RT). Patients on the comparator arm received cisplatin (P) 100 mg/m2 on Day 1, followed by fluorouracil (F) 1000 mg/m2/day as a continuous infusion on Days 1–5. The cycles were repeated every three weeks for 4 cycles. Patients whose disease did not progress received RT according to institutional guidelines (PF/RT). At the end of chemotherapy, with a minimal interval of 4 weeks and a maximal interval of 7 weeks, patients whose disease did not progress received radiotherapy (RT) according to institutional guidelines. Locoregional therapy with radiation was delivered either with a conventional fraction regimen (1.8 Gy–2.0 Gy once a day, 5 days per week for a total dose of 66 to 70 Gy) or with an accelerated/ hyperfractionated regimen (twice a day, with a minimum interfraction interval of 6 hours, 5 days per week, for a total dose of 70 to 74 Gy, respectively). Surgical resection was allowed following chemotherapy, before or after radiotherapy.

The primary endpoint in this study, progression-free survival (PFS), was significantly longer in the TPF arm compared to the PF arm, p=0.0077 (median PFS: 11.4 vs 8.3 months, respectively) with an overall median follow-up time of 33.7 months. Median overall survival with a median follow-up of 51.2 months was also significantly longer in favor of the TPF arm compared to the PF arm (median OS: 18.6 vs 14.2 months, respectively). Efficacy results are presented in Table 20 and Figures 8 and 9.

Table 20: Efficacy of DOCIVYX in the Induction Treatment of Patients with Inoperable Locally Advanced SCCHN (Intent-to-Treat Analysis)
Endpoint | DOCIVYX + Cisplatin + Fluorouracil n=177 | Cisplatin + Fluorouracil n=181
Median progression free survival (months) (95% CI) Adjusted Hazard ratio (95% CI) *p-value | 11.4 (10.1–14.0) | 8.3 (7.4–9.1)
Median progression free survival (months) (95% CI) Adjusted Hazard ratio (95% CI) *p-value | 0.71 (0.56–0.91) 0.0077
Median survival (months) (95% CI) Hazard ratio (95% CI) †p-value | 18.6 (15.7–24.0) | 14.2 (11.5–18.7)
Median survival (months) (95% CI) Hazard ratio (95% CI) †p-value | 0.71 (0.56–0.90) 0.0055
Best overall response (CR + PR) to chemotherapy (%) (95% CI) ‡p-value | 67.8 (60.4–74.6) | 53.6 (46.0–61.0)
Best overall response (CR + PR) to chemotherapy (%) (95% CI) ‡p-value | 0.006
Best overall response (CR + PR) to stud treatment [chemotherapy +/- radiotherapy] (%) (95% CI) ‡p-value | 72.3 (65.1–78.8) | 58.6 (51.0–65.8)
Best overall response (CR + PR) to stud treatment [chemotherapy +/- radiotherapy] (%) (95% CI) ‡p-value | 0.006
A Hazard ratio of less than 1 favors DOCIVYX+cisplatin+fluorouracil
* Stratified log- rank test based on primary tumor site
† Stratified log- rank test, not adjusted for multiple comparisons
‡ Chi square test, not adjusted for multiple comparisons

Figure 8: TAX323 Progression-Free Survival K-M Curve
Figure 9: TAX323 Overall Survival K-M Curve

Induction Chemotherapy Followed by Chemoradiotherapy (TAX324)

The safety and efficacy of DOCIVYX in the induction treatment of patients with locally advanced (unresectable, low surgical cure, or organ preservation) SCCHN was evaluated in a randomized, multicenter open-label trial (TAX324). In this study, 501 patients, with locally advanced SCCHN, and a WHO performance status of 0 or 1, were randomized to one of two treatment arms. Patients on the DOCIVYX arm received DOCIVYX (T) 75 mg/m^2 by intravenous infusion on day 1 followed by cisplatin (P) 100 mg/m^2 administered as a 30-minute to three-hour intravenous infusion, followed by the continuous intravenous infusion of fluorouracil (F) 1000 mg/m^2/day from day 1 to day 4. The cycles were repeated every 3 weeks for 3 cycles. Patients on the comparator arm received cisplatin (P) 100 mg/m^2 as a 30-minute to three-hour intravenous infusion on day 1 followed by the continuous intravenous infusion of fluorouracil (F) 1000 mg/m2/day from day 1 to day 5. The cycles were repeated every 3 weeks for 3 cycles.

All patients in both treatment arms who did not have progressive disease were to receive 7 weeks of chemoradiotherapy (CRT) following induction chemotherapy 3 to 8 weeks after the start of the last cycle. During radiotherapy, carboplatin (AUC 1.5) was given weekly as a one-hour intravenous infusion for a maximum of 7 doses. Radiation was delivered with megavoltage equipment using once daily fractionation (2 Gy per day, 5 days per week for 7 weeks for a total dose of 70–72 Gy). Surgery on the primary site of disease and/or neck could be considered at anytime following completion of CRT.

The primary efficacy endpoint, overall survival (OS), was significantly longer (log-rank test, p=0.0058) with the DOCIVYX -containing regimen compared to PF (median OS: 70.6 vs 30.1 months, respectively, hazard ratio [HR]=0.70, 95% confidence interval [CI]=0.54–0.90). Overall survival results are presented in Table 21 and Figure 10.

Table 21: Efficacy of DOCIVYX in the Induction Treatment of Patients with Locally Advanced SCCHN (Intent-to-Treat Analysis)
Endpoint | DOCIVYX + Cisplatin + Fluorouracil n=255 | Cisplatin + Fluorouracil n=246
Median overall survival (months) (95% CI) | 70.6 (49.0–NE) | 30.1 (20.9–51.5)
Hazard ratio: (95% CI) *p-value | 0.70 (0.54–0.90) 0.0058
A Hazard ratio of less than 1 favors DOCIVYX+cisplatin+fluorouracil
* unadjusted log- rank test
NE - not estimable

Figure 10: TAX324 Overall Survival K-M Curve

15 REFERENCES

1. "OSHA Hazardous Drugs." http://www.osha.gov/SLTC/hazardousdrugs/index.html

16 HOW SUPPLIED/STORAGE AND HANDLING

16.1 How Supplied

DOCIVYX® Injection is supplied in a single-dose vial as a sterile, pyrogen-free, non-aqueous, pale-yellow to brownish-yellow solution. Discard unused portion.

DOCIVYX® (docetaxel) Injection, 10 mg/mL, is available as carton of one single-dose vial in the following strengths:

20 mg/2 mL (NDC: 83831-101-02)

80 mg/8 mL (NDC: 83831-102-08)

160 mg/16 mL (NDC: 83831-103-16)

16.2 Storage

Store between 2°C and 25°C (36°F and 77°F). Retain in the original package to protect from light.

Freezing does not adversely affect the product.

16.3 Handling and Disposal

DOCIVYX is a hazardous drug. Follow applicable special handling and disposal procedures.

17 PATIENT COUNSELING INFORMATION

Advise the patient to read the FDA-approved patient labeling (Patient Information).

Bone Marrow Suppression

Advise patients that periodic assessment of their blood count will be performed to detect neutropenia, thrombocytopenia, and/ or anemia [see Contraindications (4), Warnings and Precautions (5.3)]. Instruct patients to monitor their temperature frequently and immediately report any occurrence of fever.

Enterocolitis and Neutropenic Colitis

Advise patients of the symptoms of colitis, such as abdominal pain or tenderness, and/or diarrhea, with or without fever, and instruct patients to promptly contact their healthcare provider if they experience these symptoms [see Dosage and Administration (2.7) and Warnings and Precautions (5.4)].

Hypersensitivity Reactions

Ask patients whether they have previously received paclitaxel therapy, and if they have experienced a hypersensitivity reaction to paclitaxel. Instruct patients to immediately report to their healthcare provider signs of a hypersensitivity reaction [see Contraindications (4), Warnings and Precautions (5.5)].

Fluid Retention

Advise patients to report signs of fluid retention such as peripheral edema in the lower extremities, weight gain, and dyspnea immediately to their healthcare provider [see Warnings and Precautions (5.6)].

Second Primary Malignancies

Advise patients on the risk of second primary malignancies during treatment with DOCIVYX [see Warnings and Precautions (5.7)].

Cutaneous Reactions

Advise patients that localized erythema of the extremities and severe skin toxicities may occur. Instruct patients to immediately report severe cutaneous reactions to their healthcare provider [see Dosage and Administration (2.7) and Warnings and Precautions (5.8)].

Neurologic Reactions

Advise patients that neurosensory symptoms or peripheral neuropathy may occur. Instruct patients to immediately report neurologic reactions to their healthcare provider [see Dosage and Administration (2.7) and Warnings and Precautions (5.9)].

Eye Disorders

Advise patients that vision disturbances and excessive tearing are associated with DOCIVYX administration. Instruct patients to immediately report any vision changes to their healthcare provider [see Warnings and Precautions (5.10)].

Gastrointestinal Reactions

Explain to patients that nausea, vomiting, diarrhea, and constipation are associated with DOCIVYX administration. Instruct patients to report any severe events to their healthcare provider [see Adverse Reactions (6)].

Cardiac Disorders

Advise patients to report any irregular and/or rapid heartbeat, severe shortness of breath, dizziness, and/or fainting immediately to their healthcare provider [see Adverse Reactions (6)].

Other Common Adverse Reactions

Advise patients that other common adverse reactions associated with DOCIVYX may include alopecia (cases of permanent hair loss have been reported), asthenia, anorexia, dysgeusia, mucositis, myalgia, nail disorders, or pain. Instruct patients to report these reactions to their healthcare provider if serious events occur [see Adverse Reactions (6)].

Importance of Corticosteroids

Explain the significance of oral corticosteroids such as dexamethasone administration to the patient to help facilitate compliance. Instruct patients to report to their healthcare provider if they were not compliant with the oral corticosteroid regimen [see Dosage and Administration (2.6)].

Embryo-Fetal Toxicity

DOCIVYX can cause fetal harm. Advise patients to inform their healthcare provider of a known or suspected pregnancy. Advise patients to avoid becoming pregnant while receiving this drug. Advise female patients of reproductive potential to use effective contraception during treatment and for 2 months after the last dose of DOCIVYX. Advise male patients with female partners of reproductive potential to use effective contraception during treatment and for 4 months after the last dose of DOCIVYX [see Warnings and Precautions (5.12), and Use in Specific Populations (8.1, 8.3)].

Lactation

Advise women not to breastfeed during DOCIVYX treatment and for 1 week after the last dose [see Use in Specific Populations (8.2)].

Infertility

Advise males of reproductive potential that DOCIVYX may impair fertility [see Nonclinical Toxicology (13.1)].

Alcohol Content in DOCIVYX

Explain to patients the possible effects of the alcohol content in DOCIVYX, including possible effects on the central nervous system [see Warnings and Precautions (5.13)].

Tumor Lysis Syndrome

Advise patients of the potential risk of tumor lysis syndrome and to immediately report any signs or symptoms associated with this event (nausea, vomiting, confusion, shortness of breath, seizure, irregular heartbeat, dark or cloudy urine, reduced amount of urine, unusual tiredness, muscle cramps) to their healthcare provider. Advise patients of the importance of keeping scheduled appointment for blood work or other laboratory tests and of drinking adequate fluids to avoid dehydration. [see Warnings and Precautions (5.14)].

Ability to Drive or Operate Machines

Explain to patients that DOCIVYX may impair their ability to drive or operate machines due to its side effects [see Adverse Reactions (6)] or due to the alcohol content of DOCIVYX [see Warnings and Precautions (5.13)]. Advise them not to drive or use machines if they experience these side effects during treatment.

Drug Interactions

Inform patients about the risk of drug interactions and the importance of providing a list of prescription and non-prescription drugs to their healthcare provider [see Drug Interactions (7)].

Avyxa Pharma, LLC
New Jersey 07054, USA
Made in China
Rx Only

SPL PATIENT PACKAGE INSERT

Patient Information
DOCIVYX® (DOH-sih-vix)
(docetaxel) injection
for intravenous use

What is the most important information I should know about DOCIVYX ?
DOCIVYX may cause serious side effects, including death.
● The chance of death in people who receive DOCIVYX is higher if you:
o have liver problems
o receive high doses of DOCIVYX
o have non-small cell lung cancer and have been treated with chemotherapy medicines that contain platinum
● DOCIVYX can affect your blood cells. Your healthcare provider should do routine blood tests during treatment with DOCIVYX. This will include regular checks of your white blood cell counts. If your white blood cells are too low, your healthcare provider may not treat you with DOCIVYX until you have enough white blood cells. People with low white blood cell counts can develop life-threatening infections. The earliest sign of infection may be fever. Follow your healthcare provider's instructions for how often to take your temperature during treatment with DOCIVYX. Call your healthcare provider right away if you have a fever.
● Swelling (inflammation) of the small intestine and colon. This can happen at any time during treatment and could lead to death as early as the first day you get symptoms. Tell your healthcare provider right away if you develop new or worse symptoms of intestinal problems, including stomach (abdominal) pain or tenderness or diarrhea, with or without fever.
● Severe allergic reactions are medical emergencies that can happen in people who receive DOCIVYX and can lead to death. You may be at higher risk of developing a severe allergic reaction to DOCIVYX if you are allergic to paclitaxel. Your healthcare provider will monitor you closely for allergic reactions during your DOCIVYX infusion.
Tell your healthcare provider right away if you have any of these signs of a severe allergic reaction:
o trouble breathing
o sudden swelling of your face, lips, tongue, throat, or trouble swallowing
o hives (raised bumps), rash, or redness all over your body
● Your body may hold too much fluid (severe fluid retention) during treatment with DOCIVYX. This can be life threatening. To decrease the chance of this happening, you must take another medicine, a corticosteroid, before each DOCIVYX treatment. You must take the corticosteroid exactly as your healthcare provider tells you. Tell your healthcare provider or nurse before your DOCIVYX treatment if you forgot to take your corticosteroid dose or do not take it as your healthcare provider tells you. Tell your healthcare provider right away if you have swelling in your legs or feet, weight gain or shortness of breath.
● Risk of new cancers. An increase in new (second) cancers has happened in people treated with DOCIVYX together with certain other anticancer treatments. This includes certain blood cancers, such as acute myeloid leukemia (AML), myelodysplastic syndrome (MDS), non-Hodgkin's Lymphoma (NHL), and kidney cancer.

- Changes in blood counts due to leukemia and other blood disorders may occur years after treatment with DOCIVYX.

Your healthcare provider will check you for new cancers during and after your treatment with DOCIVYX.
● Severe skin problems.
Tell your healthcare provider right away if you have any of these signs of a severe skin reaction:

- redness and swelling of your arms and legs.
- blistering, peeling, or bleeding on any part of your skin (including your lips, eyes, mouth, nose, genitals, hands or feet) with or without a rash. You may also have flu-like symptoms such as fever, chills, or muscle aches.
- red, scaly rash all over your body with blisters, small red or white bumps under the skin that contain pus (pustules), and fever.

What is DOCIVYX ?
DOCIVYX is a prescription anticancer medicine used to treat certain people with:
● breast cancer
● non-small cell lung cancer
● prostate cancer
● stomach cancer
● head and neck cancer
It is not known if DOCIVYX is effective in children.

Do not receive DOCIVYX if you:
● have a low white blood cell count.
● have had a severe allergic reaction to docetaxel, the active ingredient in DOCIVYX.
See "What is the most important information I should know about DOCIVYX ? " for the signs and symptoms of a severe allergic reaction.
See the end of this Patient Information for a complete list of the ingredients in DOCIVYX.

Before you receive DOCIVYX , tell your healthcare provider about all of your medical conditions, including if you:
● are allergic to any medicines, including paclitaxel. See " Do not receive DOCIVYX if you ".
● have liver problems
● have kidney problems
● are pregnant or plan to become pregnant. DOCIVYX can harm your unborn baby. You should not become pregnant during treatment with DOCIVYX. Tell your healthcare provider if you become pregnant or you think you may be pregnant during treatment with DOCIVYX.
Females who are able to become pregnant:
o Your healthcare provider will check to see if you are pregnant before you start treatment with
DOCIVYX.
o You should use effective birth control (contraception) during treatment with DOCIVYX and for 2 months after the last dose.
Males with female partners who are able to become pregnant should use effective birth control during treatment with DOCIVYX and for 4 months after the last dose.
Talk to your healthcare provider if you have questions about birth control options that are right for you.
● are breastfeeding or plan to breastfeed. It is not known if DOCIVYX passes into your breast milk. Do not breastfeed during treatment with DOCIVYX and for 1 week after the last dose.
Tell your healthcare provider about all the medicines you take, including prescription and over-the-counter medicines, vitamins, and herbal supplements. DOCIVYX may affect the way other medicines work, and other medicines may affect the way DOCIVYX works.
Know the medicines you take. Keep a list of them to show your healthcare provider and pharmacist when you get a new medicine.

How will I receive DOCIVYX ?
● DOCIVYX will be given to you as an intravenous (IV) injection into your vein, usually over 1 hour.
● DOCIVYX is usually given every 3 weeks.
● Your healthcare provider will decide how long you will receive treatment with DOCIVYX.
● Your healthcare provider will check your blood cell counts and other blood tests during your treatment with DOCIVYX to check for side effects of DOCIVYX.
● Your healthcare provider may stop your treatment, change the timing of your treatment, or change the dose of your treatment if you have certain side effects while receiving DOCIVYX.

What are the possible side effects of DOCIVYX ?
DOCIVYX may cause serious side effects including death.
● See "What is the most important information I should know about DOCIVYX ?"
● Neurologic problems. Neurologic symptoms are common in people who receive DOCIVYX but can be severe. Tell your healthcare provider right away if you have numbness, tingling, or burning in your hands or feet (peripheral neuropathy) or weakness of your legs, feet, arms, or hands (motor weakness).
● Vision problems including blurred vision or loss of vision. Tell your healthcare provider right away if you have any vision changes.
● DOCIVYX contains alcohol. The alcohol content in DOCIVYX may impair your ability to drive or use machinery right after receiving DOCIVYX. Consider whether you should drive, operate machinery or do other dangerous activities right after you receive DOCIVYX treatment.
● Tumor lysis syndrome (TLS). TLS is caused by the fast breakdown of cancer cells. TLS can cause kidney failure, the need for dialysis treatment, or heart problems, and may lead to death. Your healthcare provider will do blood tests to check for TLS when you first start treatment and during treatment with DOCIVYX. Tell your healthcare provider right away if you have any symptoms of TLS during treatment with DOCIVYX, including:
○ nausea
○ vomiting
○ confusion
○ shortness of breath
○ irregular heartbeat
○ dark or cloudy urine
○ reduced amount of urine
○ unusual tiredness
○ muscle cramps
● You may experience side effects of this medicine that may impair your ability to drive, use tools, or operate machines. If this happens, do not drive or use any tools or machines before discussing with your healthcare provider.
The most common side effects of DOCIVYX include:
● infections
● low white blood cells (help fight infections), low red blood cells (anemia), and low platelets (help blood to clot)
● allergic reactions (See "What is the most important information I should know about DOCIVYX ?")
● changes in your sense of taste
● shortness of breath
● constipation
● decreased appetite
● changes in your fingernails or toenails
● swelling of your hands, face or feet
● feeling weak or tired
● joint and muscle pain
● nausea and vomiting
● diarrhea
● mouth or lip sores
● hair loss: in some people, permanent hair loss has been reported
● redness of the eye, excess tearing
● skin reactions at the site of Docetaxel Injection administration such as increased skin pigmentation, redness, tenderness, swelling, warmth or dryness of the skin
● tissue damage if Docetaxel Injection leaks out of the vein into the tissues
Tell your healthcare provider if you have a fast or irregular heartbeat, severe shortness of breath, dizziness or fainting during your infusion. If any of these events occurs after your infusion, get medical help right away.
DOCIVYX may affect fertility in males. Talk to your healthcare provider if this is a concern for you.
These are not all the possible side effects of DOCIVYX. For more information, ask your healthcare provider or pharmacist.
Call your doctor for medical advice about side effects. You may report side effects to FDA at 1-800-FDA-1088.

General information about the safe and effective use of DOCIVYX .
Medicines are sometimes prescribed for purposes other than those listed in this Patient Information. You can ask your pharmacist or healthcare provider for information about DOCIVYX that is written for health professionals

What are the ingredients in DOCIVYX ?
Active ingredient: docetaxel
Inactive ingredients: sulfoxybutyl ether cyclodextrin (SBECD), polyethyleneglycol 300, polyvinyl pyrroldine K12, and dehydrated alcohol in water for injection, with citric acid for pH adjustment.

Manufactured for:
Avyxa Pharma, LLC
New Jersey 07054, USA
Made in China
Rx Only
For more information, call 1-888-520-0954.

This Patient Information has been approved by the U.S. Food and Drug Administration. Issued: January 2025

Every three-week injection of for DOCIVYX breast, non-small cell lung and stomach, and head and neck cancers
Take your oral corticosteroid medicine as your healthcare provider tells you.
Oral corticosteroid dosing:
Day 1 Date: _________ Time: _________ AM _________PM
Day 2 Date: _________ Time: _________ AM _________PM
(DOCIVYX Treatment Day)
Day 3 Date: _________ Time: _________ AM _________PM

Every three-week injection of DOCIVYX for prostate cancer
Take your oral corticosteroid medicine as your healthcare provider tells you.
Oral corticosteroid dosing:
Date: _________ Time: ___________
Date: _________ Time: ___________
(DOCIVYX Treatment Day)
Time: ___________

PACKAGE LABEL.PRINCIPAL DISPLAY PANEL

DOCIVYX (docetaxel) Injection, 20 mg/2 mL -Vial Label
DOCIVYX (docetaxel) Injection, 20 mg/2 mL -Carton Label
DOCIVYX (docetaxel) Injection, 80 mg/8 mL -Vial Label
DOCIVYX (docetaxel) Injection, 80 mg/8 mL -Carton Label
DOCIVYX (docetaxel) Injection, 160 mg/16 mL -Vial Label
DOCIVYX (docetaxel) Injection, 160 mg/16 mL -Carton Label